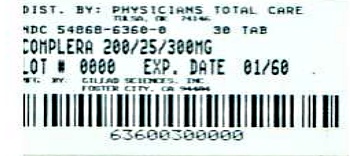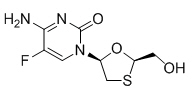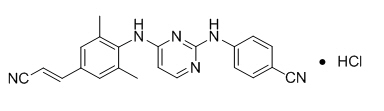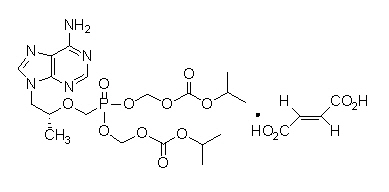 DRUG LABEL: COMPLERA
NDC: 54868-6360 | Form: TABLET, FILM COATED
Manufacturer: Physicians Total Care, Inc.
Category: prescription | Type: HUMAN PRESCRIPTION DRUG LABEL
Date: 20130315

ACTIVE INGREDIENTS: emtricitabine 200 mg/1 1; rilpivirine hydrochloride 25 mg/1 1; tenofovir disoproxil fumarate 300 mg/1 1
INACTIVE INGREDIENTS: cellulose, microcrystalline; lactose monohydrate; Povidones; polysorbate 20; croscarmellose sodium; magnesium stearate; starch, corn; hypromelloses; FD&C Blue No. 2; aluminum oxide; polyethylene glycols; ferric oxide red; FD&C Yellow No. 6; titanium dioxide; triacetin

HIGHLIGHTS OF PRESCRIBING INFORMATION

These highlights do not include all the information needed to use COMPLERA safely and effectively. See full prescribing information for COMPLERA.
COMPLERA® (emtricitabine/rilpivirine/tenofovir disoproxil fumarate) tablets, for oral use
Initial U.S. Approval: 2011

WARNING: LACTIC ACIDOSIS/SEVERE HEPATOMEGALY WITH STEATOSIS and POST TREATMENT ACUTE EXACERBATION OF HEPATITIS B

See full prescribing information for complete boxed warning.

- Lactic acidosis and severe hepatomegaly with steatosis, including fatal cases, have been reported with the use of nucleoside analogs, including tenofovir disoproxil fumarate, a component of COMPLERA. (5.1)
- COMPLERA is not approved for the treatment of chronic hepatitis B virus (HBV) infection. Severe acute exacerbations of hepatitis B have been reported in patients coinfected with HIV-1 and HBV who have discontinued EMTRIVA or VIREAD, two of the components of COMPLERA. Hepatic function should be monitored closely in these patients. If appropriate, initiation of anti-hepatitis B therapy may be warranted. (5.2)

RECENT MAJOR CHANGES

Indications and Usage (1) | 01/2013
Contraindications (4) | 01/2013
Warnings and Precautions
Depressive Disorders (5.5) | 01/2013
Hepatotoxicity (5.6) | 01/2013
Coadministration with Other Products (5.8) | 01/2013
Immune Reconstitution Syndrome (5.10) | 08/2012

1 INDICATIONS AND USAGE

COMPLERA, a combination of 2 nucleoside analog HIV-1 reverse transcriptase inhibitors (emtricitabine and tenofovir disoproxil fumarate) and 1 non-nucleoside reverse transcriptase inhibitor (rilpivirine), is indicated for use as a complete regimen for the treatment of HIV-1 infection in treatment-naive adult patients with HIV-1 RNA less than or equal to 100,000 copies/mL. (1)

This indication is based on safety and efficacy analyses through 96 weeks from 2 randomized, double-blind, active controlled, Phase 3 trials in treatment-naïve subjects. (14)

The following points should be considered when initiating therapy with COMPLERA:

- More rilpivirine-treated subjects with HIV-1 RNA greater than 100,000 copies/mL at the start of therapy experienced virologic failure (HIV-1 RNA ≥50 copies/mL) compared to rilpivirine-treated subjects with HIV-1 RNA less than or equal to 100,000 copies/mL.
- Regardless of HIV-1 RNA level at the start of therapy, more rilpivirine-treated subjects with CD4+ cell count less than 200 cells/mm^3 at the start of therapy experienced virologic failure compared to subjects with CD4+ cell count greater than or equal to 200 cells/mm^3.
- The observed virologic failure rate in rilpivirine-treated subjects conferred a higher rate of overall treatment resistance and cross-resistance to the NNRTI class compared to efavirenz.
- More subjects treated with rilpivirine developed tenofovir and lamivudine/emtricitabine associated resistance compared to efavirenz. (1, 12.4, 14)
- COMPLERA is not recommended for patients less than 18 years of age. (8.4)

2 DOSAGE AND ADMINISTRATION

- Recommended dose: One tablet (containing 200 mg of emtricitabine, 25 mg of rilpivirine, and 300 mg of tenofovir disoproxil fumarate) taken once daily with a meal. (2)
- Dose in renal impairment: Should not be administered in patients with creatinine clearance below 50 mL per minute. (2)

3 DOSAGE FORMS AND STRENGTHS

Tablets: 200 mg of emtricitabine, 25 mg of rilpivirine, and 300 mg of tenofovir disoproxil fumarate. (3)

4 CONTRAINDICATIONS

Coadministration of COMPLERA is contraindicated with drugs where significant decreases in rilpivirine plasma concentrations may occur, which may result in loss of virologic response and possible resistance and cross-resistance. (4)

5 WARNINGS AND PRECAUTIONS

- New onset or worsening renal impairment: Can include acute renal failure and Fanconi syndrome. Assess creatinine clearance (CrCl) before initiating treatment with COMPLERA. Monitor CrCl and serum phosphorus in patients at risk. Avoid administering COMPLERA with concurrent or recent use of nephrotoxic drugs. (5.3)
- Caution should be given to prescribing COMPLERA with drugs that may reduce the exposure of rilpivirine. (5.4)
- Caution should be given to prescribing COMPLERA with drugs with a known risk of Torsade de Pointes. (5.4)
- Depressive disorders: Severe depressive disorders have been reported. Immediate medical evaluation is recommended for severe depressive disorders. (5.5)
- Hepatotoxicity: Hepatic adverse events have been reported in patients receiving a rilpivirine-containing regimen. Monitor serum liver biochemistries before and during treatment with COMPLERA in patients with underlying hepatic disease or marked elevations in serum liver biochemistries. Also consider monitoring serum liver biochemistries in patients without risk factors. (5.6)
- Decreases in bone mineral density (BMD): Consider monitoring BMD in patients with a history of pathologic fracture or other risk factors of osteoporosis or bone loss. (5.7)
- Coadministration with other products: Do not use with drugs containing emtricitabine, rilpivirine or tenofovir disoproxil fumarate including ATRIPLA, EDURANT, EMTRIVA, STRIBILD, TRUVADA, VIREAD, or with drugs containing lamivudine. Do not administer in combination with HEPSERA. (5.8)
- Redistribution/accumulation of body fat: Observed in patients receiving antiretroviral therapy. (5.9)
- Immune reconstitution syndrome: May necessitate further evaluation and treatment. (5.10)

6 ADVERSE REACTIONS

Most common adverse drug reactions to rilpivirine (incidence greater than or equal to 2%, Grades 2–4) are depressive disorders, insomnia, and headache. (6.1)

Most common adverse drug reactions to emtricitabine and tenofovir disoproxil fumarate (incidence ≥10%) are diarrhea, nausea, fatigue, headache, dizziness, depression, insomnia, abnormal dreams, and rash. (6.1)

To report SUSPECTED ADVERSE REACTIONS, contact Gilead Sciences, Inc. at 1-800-GILEAD-5 or FDA at 1-800-FDA-1088 or www.fda.gov/medwatch

7 DRUG INTERACTIONS

- COMPLERA is a complete regimen for the treatment of HIV-1 infection; therefore, COMPLERA should not be administered with other antiretroviral medications for treatment of HIV-1 infection.
- CYP3A4 inducers or inhibitors: Drugs that induce or inhibit CYP3A4 may affect the plasma concentrations of rilpivirine. (7.1)
- Drugs that increase gastric pH: Drugs that increase gastric pH may decrease plasma concentrations of rilpivirine. (7.2)

8 USE IN SPECIFIC POPULATIONS

- Pregnancy: Use during pregnancy only if the potential benefit justifies the potential risk. (8.1)
- Nursing mothers: Women infected with HIV should be instructed not to breastfeed due to the potential for HIV transmission. (8.3)
- Pediatrics: Not recommended for patients less than 18 years of age. (8.4)

FULL PRESCRIBING INFORMATION

WARNING: LACTIC ACIDOSIS/SEVERE HEPATOMEGALY WITH STEATOSIS and POST TREATMENT ACUTE EXACERBATION OF HEPATITIS B

Lactic acidosis and severe hepatomegaly with steatosis, including fatal cases, have been reported with the use of nucleoside analogs, including tenofovir disoproxil fumarate, a component of COMPLERA, in combination with other antiretrovirals [See Warnings and Precautions (5.1)].

COMPLERA is not approved for the treatment of chronic hepatitis B virus (HBV) infection and the safety and efficacy of COMPLERA have not been established in patients coinfected with HBV and HIV-1. Severe acute exacerbations of hepatitis B have been reported in patients who are coinfected with HBV and HIV-1 and have discontinued EMTRIVA or VIREAD, which are components of COMPLERA. Hepatic function should be monitored closely with both clinical and laboratory follow-up for at least several months in patients who are coinfected with HIV-1 and HBV and discontinue COMPLERA. If appropriate, initiation of anti-hepatitis B therapy may be warranted [See Warnings and Precautions (5.2)].

1 INDICATIONS AND USAGE

COMPLERA® (emtricitabine/rilpivirine/tenofovir disoproxil fumarate) is indicated for use as a complete regimen for the treatment of HIV-1 infection in antiretroviral treatment-naive adult patients with HIV-1 RNA less than or equal to 100,000 copies/mL at the start of therapy.

This indication is based on safety and efficacy analyses through 96 weeks from 2 randomized, double-blind, active controlled, Phase 3 trials in treatment-naive subjects comparing rilpivirine to efavirenz [See Clinical Studies (14)].

The following points should be considered when initiating therapy with COMPLERA:

- More rilpivirine-treated subjects with HIV-1 RNA greater than 100,000 copies/mL at the start of therapy experienced virologic failure (HIV-1 RNA ≥50 copies/mL) compared to rilpivirine-treated subjects with HIV-1 RNA less than or equal to 100,000 copies/mL [See Clinical Studies (14)].
- Regardless of HIV-1 RNA level at the start of therapy, more rilpivirine-treated subjects with CD4+ cell count less than 200 cells/mm^3 experienced virologic failure compared to rilpivirine-treated subjects with CD4+ cell count greater than or equal to 200 cells/mm^3 [See Clinical Studies (14)].
- The observed virologic failure rate in rilpivirine-treated subjects conferred a higher rate of overall treatment resistance and cross-resistance to the NNRTI class compared to efavirenz [See Microbiology (12.4)].
- More subjects treated with rilpivirine developed tenofovir and lamivudine/emtricitabine associated resistance compared to efavirenz [See Microbiology (12.4)].

COMPLERA is not recommended for patients less than 18 years of age [See Use in Specific Populations (8.4)].

2 DOSAGE AND ADMINISTRATION

Adults: The recommended dose of COMPLERA is one tablet taken orally once daily with a meal [See Clinical Pharmacology (12.3)].

Renal Impairment: Because COMPLERA is a fixed-dose combination, it should not be prescribed for patients requiring dose adjustment such as those with moderate or severe renal impairment (creatinine clearance below 50 mL per minute).

3 DOSAGE FORMS AND STRENGTHS

COMPLERA is available as tablets. Each tablet contains 200 mg of emtricitabine (FTC), 27.5 mg of rilpivirine hydrochloride (equivalent to 25 mg of rilpivirine) and 300 mg of tenofovir disoproxil fumarate (tenofovir DF or TDF, equivalent to 245 mg of tenofovir disoproxil).

The tablets are purplish-pink, capsule-shaped, film-coated, debossed with "GSI" on one side and plain-faced on the other side.

4 CONTRAINDICATIONS

COMPLERA should not be coadministered with the following drugs, as significant decreases in rilpivirine plasma concentrations may occur due to CYP3A enzyme induction or gastric pH increase, which may result in loss of virologic response and possible resistance to COMPLERA or to the class of NNRTIs [See Drug Interactions (7) and Clinical Pharmacology (12.3)]:

- the anticonvulsants carbamazepine, oxcarbazepine, phenobarbital, phenytoin
- the antimycobacterials rifabutin, rifampin, rifapentine
- proton pump inhibitors, such as dexlansoprazole, esomeprazole, lansoprazole, omeprazole, pantoprazole, rabeprazole
- the glucocorticoid systemic dexamethasone (more than a single dose)
- St. John's wort (Hypericum perforatum)

5 WARNINGS AND PRECAUTIONS

5.1 Lactic Acidosis/Severe Hepatomegaly with Steatosis

Lactic acidosis and severe hepatomegaly with steatosis, including fatal cases, have been reported with the use of nucleoside analogs, including tenofovir DF, a component of COMPLERA, in combination with other antiretrovirals. A majority of these cases have been in women. Obesity and prolonged nucleoside exposure may be risk factors. Particular caution should be exercised when administering nucleoside analogs to any patient with known risk factors for liver disease; however, cases have also been reported in patients with no known risk factors. Treatment with COMPLERA should be suspended in any patient who develops clinical or laboratory findings suggestive of lactic acidosis or pronounced hepatotoxicity (which may include hepatomegaly and steatosis even in the absence of marked transaminase elevations).

5.2 Patients Coinfected with HIV-1 and HBV

It is recommended that all patients with HIV-1 be tested for the presence of chronic hepatitis B virus before initiating antiretroviral therapy. COMPLERA is not approved for the treatment of chronic HBV infection and the safety and efficacy of COMPLERA have not been established in patients coinfected with HBV and HIV-1. Severe acute exacerbations of hepatitis B have been reported in patients who are coinfected with HBV and HIV-1 and have discontinued emtricitabine or tenofovir DF, two of the components of COMPLERA. In some patients infected with HBV and treated with EMTRIVA®, the exacerbations of hepatitis B were associated with liver decompensation and liver failure. Patients who are coinfected with HIV-1 and HBV should be closely monitored with both clinical and laboratory follow-up for at least several months after stopping treatment with COMPLERA. If appropriate, initiation of anti-hepatitis B therapy may be warranted.

5.3 New Onset or Worsening Renal Impairment

Renal impairment, including cases of acute renal failure and Fanconi syndrome (renal tubular injury with severe hypophosphatemia), has been reported with the use of tenofovir DF [See Adverse Reactions (6.2)].

It is recommended that creatinine clearance be calculated in all patients prior to initiating therapy and as clinically appropriate during therapy with COMPLERA. Routine monitoring of calculated creatinine clearance and serum phosphorus should be performed in patients at risk for renal impairment, including patients who have previously experienced renal events while receiving HEPSERA®.

COMPLERA should be avoided with concurrent or recent use of a nephrotoxic agent.

Emtricitabine and tenofovir are principally eliminated by the kidney; however, rilpivirine is not. Since COMPLERA is a combination product and the dose of the individual components cannot be altered, patients with creatinine clearance below 50 mL per minute should not receive COMPLERA.

5.4 Drug Interactions

Caution should be given to prescribing COMPLERA with drugs that may reduce the exposure of rilpivirine [See Contraindications (4), Drug Interactions (7), and Clinical Pharmacology (12.3)].

In healthy subjects, supratherapeutic doses of rilpivirine (75 mg once daily and 300 mg once daily) have been shown to prolong the QTc interval of the electrocardiogram [See Drug Interactions (7) and Clinical Pharmacology (12.2)]. COMPLERA should be used with caution when coadministered with a drug with a known risk of Torsade de Pointes.

5.5 Depressive Disorders

The adverse reaction depressive disorders (depressed mood, depression, dysphoria, major depression, mood altered, negative thoughts, suicide attempt, suicidal ideation) has been reported with rilpivirine. During the Phase 3 trials (N=1368) through 96 weeks, the incidence of depressive disorders (regardless of causality, severity) reported among rilpivirine (N=686) or efavirenz (N=682) was 9% and 8%, respectively. Most events were mild or moderate in severity. The incidence of Grade 3 and 4 depressive disorders (regardless of causality) was 1% for both rilpivirine and efavirenz. The incidence of discontinuation due to depressive disorders among rilpivirine or efavirenz was 1% in each arm. Suicidal ideation was reported in 4 subjects in each arm while suicide attempt was reported in 2 subjects in the rilpivirine arm. Patients with severe depressive symptoms should seek immediate medical evaluation to assess the possibility that the symptoms are related to COMPLERA, and if so, to determine whether the risks of continued therapy outweigh the benefits.

5.6 Hepatotoxicity

Hepatic adverse events have been reported in patients receiving a rilpivirine containing regimen. Patients with underlying hepatitis B or C, or marked elevations in serum liver biochemistries prior to treatment may be at increased risk for worsening or development of serum liver biochemistries elevations with use of COMPLERA. A few cases of hepatic toxicity have been reported in patients receiving a rilpivirine containing regimen who had no pre-existing hepatic disease or other identifiable risk factors. Appropriate laboratory testing prior to initiating therapy and monitoring for hepatotoxicity during therapy with COMPLERA is recommended in patients with underlying hepatic disease such as hepatitis B or C, or in patients with marked elevations in serum liver biochemistries prior to treatment initiation. Serum liver biochemistries monitoring should also be considered for patients without pre-existing hepatic dysfunction or other risk factors.

5.7 Decreases in Bone Mineral Density

Bone mineral density (BMD) monitoring should be considered for HIV-1 infected patients who have a history of pathologic bone fracture or other risk factors for osteoporosis or bone loss. Although the effect of supplementation with calcium and Vitamin D was not studied, such supplementation may be beneficial for all patients. If bone abnormalities are suspected then appropriate consultation should be obtained.

Tenofovir Disoproxil Fumarate: In a 144 week study of HIV-1 infected treatment-naive adult subjects treated with tenofovir DF (Study 903), decreases in BMD were seen at the lumbar spine and hip in both arms of the study. At Week 144, there was a significantly greater mean percentage decrease from baseline in BMD at the lumbar spine in subjects receiving tenofovir DF + lamivudine + efavirenz (-2.2% ± 3.9) compared with subjects receiving stavudine + lamivudine + efavirenz (-1.0% ± 4.6). Changes in BMD at the hip were similar between the two treatment groups (-2.8% ± 3.5 in the tenofovir DF group vs. -2.4% ± 4.5 in the stavudine group). In both groups, the majority of the reduction in BMD occurred in the first 24–48 weeks of the study and this reduction was sustained through 144 weeks. Twenty-eight percent of tenofovir DF-treated subjects vs. 21% of the comparator subjects lost at least 5% of BMD at the spine or 7% of BMD at the hip. Clinically relevant fractures (excluding fingers and toes) were reported in 4 subjects in the tenofovir DF group and 6 subjects in the comparator group. Tenofovir DF was associated with significant increases in biochemical markers of bone metabolism (serum bone-specific alkaline phosphatase, serum osteocalcin, serum C telopeptide, and urinary N telopeptide), suggesting increased bone turnover. Serum parathyroid hormone levels and 1,25 Vitamin D levels were also higher in subjects receiving tenofovir DF.

The effects of tenofovir DF-associated changes in BMD and biochemical markers on long-term bone health and future fracture risk are unknown. For additional information, please consult the VIREAD® prescribing information.

Cases of osteomalacia (associated with proximal renal tubulopathy and which may contribute to fractures) have been reported in association with the use of VIREAD [See Adverse Reactions (6.2)].

5.8 Coadministration with Other Products

COMPLERA should not be administered concurrently with other medicinal products containing any of the same active components, emtricitabine, rilpivirine, or tenofovir DF (ATRIPLA®, Edurant®, EMTRIVA, STRIBILD™, TRUVADA®, VIREAD), with medicinal products containing lamivudine (Epivir®, Epivir-HBV®, Epzicom®, Combivir®, Trizivir®), or with adefovir dipivoxil (HEPSERA).

5.9 Fat Redistribution

Redistribution/accumulation of body fat including central obesity, dorsocervical fat enlargement (buffalo hump), peripheral wasting, facial wasting, breast enlargement, and "cushingoid appearance" have been observed in patients receiving antiretroviral therapy. The mechanism and long-term consequences of these events are unknown. A causal relationship has not been established.

5.10 Immune Reconstitution Syndrome

Immune reconstitution syndrome has been reported in patients treated with combination antiretroviral therapy, including the components of COMPLERA. During the initial phase of combination antiretroviral treatment, patients whose immune system responds may develop an inflammatory response to indolent or residual opportunistic infections [such as Mycobacterium avium infection, cytomegalovirus, Pneumocystis jirovecii pneumonia (PCP), or tuberculosis], which may necessitate further evaluation and treatment.

Autoimmune disorders (such as Graves' disease, polymyositis, and Guillain-Barré syndrome) have also been reported to occur in the setting of immune reconstitution, however, the time to onset is more variable, and can occur many months after initiation of treatment.

6 ADVERSE REACTIONS

The following adverse drug reactions are discussed in other sections of the labeling:

- Lactic Acidosis/Severe Hepatomegaly with Steatosis [See Boxed Warning, Warnings and Precautions (5.1)].
- Severe Acute Exacerbations of Hepatitis B [See Boxed Warning, Warnings and Precautions (5.2)].
- New Onset or Worsening Renal Impairment [See Warnings and Precautions (5.3)].
- Depressive Disorders [See Warnings and Precautions (5.5)].
- Hepatotoxicity [See Warnings and Precautions (5.6)].
- Decreases in Bone Mineral Density [See Warnings and Precautions (5.7)].
- Immune Reconstitution Syndrome [See Warnings and Precautions (5.10)].

6.1 Adverse Reactions from Clinical Trials Experience

Because clinical trials are conducted under widely varying conditions, adverse reaction rates observed in the clinical trials of a drug cannot be directly compared to rates in the clinical trials of another drug and may not reflect the rates observed in practice.

Studies C209 and C215 – Treatment-Emergent Adverse Drug Reactions: The safety assessment of rilpivirine, used in combination with other antiretroviral drugs, is based on the Week 96 pooled data from 1368 subjects in the Phase 3 trials TMC278-C209 (ECHO) and TMC278-C215 (THRIVE) in antiretroviral treatment-naive HIV-1 infected adult subjects. A total of 686 subjects received rilpivirine in combination with other antiretroviral drugs as background regimen; most (N=550) received emtricitabine/tenofovir DF as background regimen. The number of subjects randomized to the control arm efavirenz was 682, of which 546 received emtricitabine/tenofovir DF as background regimen [See Clinical Studies (14)]. The median duration of exposure for subjects in either treatment arm was 104 weeks.

Adverse drug reactions (ADR) observed at Week 96 in subjects who received rilpivirine or efavirenz plus emtricitabine/tenofovir DF as background regimen are shown in Table 1. No new types of adverse reactions were identified between Week 48 and Week 96. The adverse drug reactions observed in this subset of subjects were generally consistent with those seen for the overall patient population participating in these studies (refer to the prescribing information for EDURANT).

The proportion of subjects who discontinued treatment with rilpivirine or efavirenz + emtricitabine/tenofovir DF due to ADR, regardless of severity, was 2% and 5%, respectively. The most common ADRs leading to discontinuation were psychiatric disorders: 9 (1.6%) subjects in the rilpivirine + emtricitabine/tenofovir DF arm and 12 (2.2%) subjects in the efavirenz + emtricitabine/tenofovir DF arm. Rash led to discontinuation in 1 (0.2%) subjects in the rilpivirine + emtricitabine/tenofovir DF arm and 10 (1.8%) subjects in the efavirenz + emtricitabine/tenofovir DF arm.

Common Adverse Drug Reactions

Clinical ADRs to rilpivirine or efavirenz of at least moderate intensity (≥ Grade 2) reported in at least 2% of adult subjects are shown in Table 1.

Table 1 Selected Treatment-Emergent Adverse Drug Reactions (Grades 2–4) Reported in ≥2% of Subjects Receiving Rilpivirine or Efavirenz in Combination with Emtricitabine/Tenofovir DF in Studies C209 and C215 (Week 96 analysis)
 | Rilpivirine + FTC/TDF | Efavirenz + FTC/TDF
 | N=550 | N=546
Gastrointestinal Disorder
Nausea | 1% | 2%
Nervous System Disorders
Headache | 2% | 2%
Dizziness | 1% | 7%
Psychiatric Disorders
Depressive disorders | 2% | 2%
Insomnia | 2% | 2%
Abnormal dreams | 1% | 3%
Skin and Subcutaneous Tissue Disorders
Rash | 1% | 5%

Rilpivirine: Treatment-emergent adverse drug reactions of at least moderate intensity (≥ Grade 2) that occurred in less than 2% of subjects treated with rilpivirine plus any of the allowed background regimens (N=686) in clinical studies C209 and C215 include (grouped by Body System): vomiting, diarrhea, abdominal discomfort, abdominal pain, fatigue, cholecystitis, cholelithiasis, decreased appetite, somnolence, sleep disorders, anxiety, glomerulonephritis membranous, glomerulonephritis mesangioproliferative, and nephrolithiasis.

Emtricitabine and Tenofovir Disoproxil Fumarate: The following adverse reactions were observed in clinical trials of emtricitabine or tenofovir DF in combination with other antiretroviral agents:

The most common adverse drug reactions occurred in at least 10% of treatment-naive subjects in a phase 3 clinical trial of emtricitabine and tenofovir DF in combination with another antiretroviral agent are diarrhea, nausea, fatigue, headache, dizziness, depression, insomnia, abnormal dreams, and rash. In addition, adverse drug reactions that occurred in at least 5% of treatment-experienced or treatment-naive subjects receiving emtricitabine or tenofovir DF with other antiretroviral agents in clinical trials include abdominal pain, dyspepsia, vomiting, fever, pain, nasopharyngitis, pneumonia, sinusitis, upper respiratory tract infection, arthralgia, back pain, myalgia, paresthesia, peripheral neuropathy (including peripheral neuritis and neuropathy), anxiety, increased cough, and rhinitis.

Skin discoloration has been reported with higher frequency among emtricitabine-treated subjects; it was manifested by hyperpigmentation on the palms and/or soles and was generally mild and asymptomatic. The mechanism and clinical significance are unknown.

Laboratory Abnormalities: The percentage of subjects treated with rilpivirine + emtricitabine/tenofovir DF or efavirenz + emtricitabine/tenofovir DF in studies C209 and C215 with selected treatment-emergent laboratory abnormalities (Grade 1 to 4), representing worst grade toxicity are presented in Table 2.

Table 2 Selected Laboratory Abnormalities (Grades 1–4) Reported in Subjects Who Received Rilpivirine or Efavirenz in Combination with Emtricitabine/Tenofovir DF in Studies C209 and C215 (Week 96 Analysis)
 |  | Rilpivirine + FTC/TDF | Efavirenz + FTC/TDF
Laboratory Parameter Abnormality, (%) | DAIDS Toxicity Range | N=550 | N=546
BIOCHEMISTRY
Increased Creatinine
Grade 1 | 1.1–1.3 × ULN | 6% | 1%
Grade 2 | >1.3–1.8 × ULN | 1% | 1%
Grade 3 | >1.8–3.4 × ULN | <1% | 0
Grade 4 | >3.4 × ULN | 0 | <1%
Increased AST
Grade 1 | 1.25–2.5 × ULN | 16% | 19%
Grade 2 | >2.5–5.0 × ULN | 4% | 7%
Grade 3 | >5.0–10.0 × ULN | 2% | 3%
Grade 4 | >10.0 × ULN | 1% | 1%
Increased ALT
Grade 1 | 1.25–2.5 × ULN | 19% | 22%
Grade 2 | >2.5–5.0 × ULN | 5% | 7%
Grade 3 | >5.0–10.0 × ULN | 1% | 2%
Grade 4 | >10.0 × ULN | 1% | 1%
Increased Total Bilirubin
Grade 1 | 1.1–1.5 × ULN | 6% | <1%
Grade 2 | >1.5–2.5 × ULN | 3% | 1%
Grade 3 | >2.5–5.0 × ULN | 1% | <1%
Increased Total Cholesterol (fasted)
Grade 1 | 200–239 mg/dL | 14% | 31%
Grade 2 | 240–300 mg/dL | 6% | 18%
Grade 3 | >300 mg/dL | <1% | 2%
Increased LDL Cholesterol (fasted)
Grade 1 | 130–159 mg/dL | 13% | 28%
Grade 2 | 160–190 mg/dL | 5% | 13%
Grade 3 | >190 mg/dL | 1% | 4%
Increased Triglycerides (fasted)
Grade 2 | 500–750 mg/dL | 1% | 2%
Grade 3 | 751–1,200 mg/dL | 1% | 2%
Grade 4 | >1,200 mg/dL | 0 | 1%
N = number of subjects per treatment group
Note: Percentages were calculated versus the number of subjects in ITT population with emtricitabine + tenofovir DF as background regimen.

Emtricitabine or Tenofovir Disoproxil Fumarate: The following laboratory abnormalities have been previously reported in subjects treated with emtricitabine or tenofovir DF with other antiretroviral agents in other clinical trials: Grade 3 or 4 laboratory abnormalities of increased pancreatic amylase (>2.0 x ULN), increased serum amylase (>175 U/L), increased lipase (>3.0 x ULN), increased alkaline phosphatase (>550 U/L), increased or decreased serum glucose (<40 or >250 mg/dL), increased glycosuria (≥3+), increased creatine kinase (M: >990 U/L; F: >845 U/L), decreased neutrophils (<750/mm^3) and increased hematuria (>75 RBC/HPF) occurred.

Adrenal Function

In the pooled Phase 3 trials of C209 and C215, in subjects treated with rilpivirine plus any of the allowed background regimen (N=686), at Week 96, there was an overall mean change from baseline in basal cortisol of -19.1 (95% CI: -30.9; -7.4) nmol/L in the rilpivirine group, and of +0.1 (95% CI: -12.6; 12.8) nmol/L in the efavirenz group. At Week 96, the mean change from baseline in ACTH-stimulated cortisol levels was lower in the rilpivirine group (+18.4± 8.36 nmol/L) than in the efavirenz group (+54.1± 7.24 nmol/L). Mean values for both basal and ACTH-stimulated cortisol values at Week 96 were within the normal range. Overall, there were no serious adverse events, deaths, or treatment discontinuations that could clearly be attributed to adrenal insufficiency. Effects on adrenal function were comparable by background N(t)RTIs.

Serum Creatinine

In the pooled Phase 3 trials of C209 and C215 trials in subjects treated with rilpivirine plus any of the allowed background regimen (N=686), there was a small increase in serum creatinine over 96 weeks of treatment with rilpivirine. Most of this increase occurred within the first four weeks of treatment with a mean change of 0.1 mg/dL (range: -0.3 mg/dL to 0.6 mg/dL) observed through Week 96. In subjects who entered the trial with mild or moderate renal impairment, the serum creatinine increase observed was similar to that seen in subjects with normal renal function. These changes are not considered to be clinically relevant and no subject discontinued treatment due to increases in serum creatinine. Creatinine increases were comparable by background N(t)RTIs.

Serum Lipids

Changes from baseline in total cholesterol, LDL-cholesterol and triglycerides are presented in Table 3.

Table 3 Lipid Values Reported in Subjects Receiving Rilpivirine or Efavirenz in Combination with Emtricitabine/Tenofovir DF in Studies C209 and C215
 | Pooled Data from the Week 96 Analysis of C209 and C215 Trials
 | Rilpivirine + FTC/TDF N=550 |  |  |  | Efavirenz + FTC/TDF N=546
 | N | Baseline | Week 96 |  | N | Baseline | Week 96
Mean |  | Mean (mg/dL) | Mean (mg/dL) | Mean Change [The change from baseline is the mean of within-patient changes from baseline for patients with both baseline and Week 96 values.] (mg/dL) |  | Mean (mg/dL) | Mean (mg/dL) | Mean Change (mg/dL)
Total Cholesterol (fasted) | 430 | 162 | 164 | 2 | 401 | 160 | 186 | 26
HDL-cholesterol (fasted) | 429 | 42 | 45 | 4 | 399 | 40 | 50 | 11
LDL-cholesterol (fasted) | 427 | 97 | 97 | -1 | 397 | 96 | 110 | 14
Triglycerides (fasted) | 430 | 123 | 109 | -14 | 401 | 127 | 133 | 6
N = number of subjects per treatment group

Subjects Coinfected with Hepatitis B and/or Hepatitis C Virus

In patients coinfected with hepatitis B or C virus receiving rilpivirine in studies C209 and C215, the incidence of hepatic enzyme elevation was higher than in subjects receiving rilpivirine who were not coinfected. The same increase was also observed in the efavirenz arm. The pharmacokinetic exposure of rilpivirine in coinfected subjects was comparable to that in subjects without coinfection.

6.2 Postmarketing Experience

The following adverse reactions have been identified during postapproval use of emtricitabine or tenofovir DF. Because postmarketing reactions are reported voluntarily from a population of uncertain size, it is not always possible to reliably estimate their frequency or establish a causal relationship to drug exposure.

Rilpivirine:

Renal and Urinary Disorders
nephrotic syndrome

Emtricitabine:

No postmarketing adverse reactions have been identified for inclusion in this section.

Tenofovir Disoproxil Fumarate:

Immune System Disorders
allergic reaction, including angioedema

Metabolism and Nutrition Disorders
lactic acidosis, hypokalemia, hypophosphatemia

Respiratory, Thoracic, and Mediastinal Disorders
dyspnea

Gastrointestinal Disorders
pancreatitis, increased amylase, abdominal pain

Hepatobiliary Disorders
hepatic steatosis, hepatitis, increased liver enzymes (most commonly AST, ALT gamma GT)

Skin and Subcutaneous Tissue Disorders
rash

Musculoskeletal and Connective Tissue Disorders
rhabdomyolysis, osteomalacia (manifested as bone pain and which may contribute to fractures), muscular weakness, myopathy

Renal and Urinary Disorders
acute renal failure, renal failure, acute tubular necrosis, Fanconi syndrome, proximal renal tubulopathy, interstitial nephritis (including acute cases), nephrogenic diabetes insipidus, renal insufficiency, increased creatinine, proteinuria, polyuria

General Disorders and Administration Site Conditions
asthenia

The following adverse reactions, listed under the body system headings above, may occur as a consequence of proximal renal tubulopathy: rhabdomyolysis, osteomalacia, hypokalemia, muscular weakness, myopathy, hypophosphatemia.

7 DRUG INTERACTIONS

COMPLERA is a complete regimen for the treatment of HIV-1 infection; therefore, COMPLERA should not be administered with other antiretroviral medications. Information regarding potential drug-drug interactions with other antiretroviral medications is not provided. Please refer to the EDURANT, VIREAD and EMTRIVA prescribing information as needed.

There were no drug-drug interaction trials conducted with the fixed-dose combination tablet. Drug interaction studies were conducted with emtricitabine, rilpivirine, or tenofovir DF, the components of COMPLERA. This section describes clinically relevant drug interactions with COMPLERA [See Contraindications (4) and Clinical Pharmacology (12.3)].

7.1 Drugs Inducing or Inhibiting CYP3A Enzymes

Rilpivirine is primarily metabolized by cytochrome P450 (CYP) 3A, and drugs that induce or inhibit CYP3A may thus affect the clearance of rilpivirine [See Clinical Pharmacology (12.3), Contraindications (4)]. Coadministration of rilpivirine and drugs that induce CYP3A may result in decreased plasma concentrations of rilpivirine and loss of virologic response and possible resistance to rilpivirine or to the class of NNRTIs. Coadministration of rilpivirine and drugs that inhibit CYP3A may result in increased plasma concentrations of rilpivirine.

Rilpivirine at a dose of 25 mg once daily is not likely to have a clinically relevant effect on the exposure of drugs metabolized by CYP enzymes.

7.2 Drugs Increasing Gastric pH

Coadministration of rilpivirine with drugs that increase gastric pH may decrease plasma concentrations of rilpivirine and loss of virologic response and possible resistance to rilpivirine or to the class of NNRTIs [See Table 4].

7.3 Drugs Affecting Renal Function

Because emtricitabine and tenofovir are primarily eliminated by the kidneys through a combination of glomerular filtration and active tubular secretion, coadministration of COMPLERA with drugs that reduce renal function or compete for active tubular secretion may increase serum concentrations of emtricitabine, tenofovir, and/or other renally eliminated drugs. Some examples of drugs that are eliminated by active tubular secretion include, but are not limited to, acyclovir, adefovir dipivoxil, cidofovir, ganciclovir, valacyclovir, and valganciclovir.

7.4 QT Prolonging Drugs

There is limited information available on the potential for a pharmacodynamic interaction between rilpivirine and drugs that prolong the QTc interval of the electrocardiogram. In a study of healthy subjects, supratherapeutic doses of rilpivirine (75 mg once daily and 300 mg once daily) have been shown to prolong the QTc interval of the electrocardiogram [See Clinical Pharmacology (12.2)]. COMPLERA should be used with caution when coadministered with a drug with a known risk of Torsade de Pointes.

7.5 Established and Other Potentially Significant Drug Interactions

Important drug interaction information for COMPLERA is summarized in Table 4. The drug interactions described are based on studies conducted with emtricitabine, rilpivirine, or tenofovir DF as individual medications that may occur with COMPLERA or are potential drug interactions; no drug interaction studies have been conducted using COMPLERA [for pharmacokinetic data see Clinical Pharmacology (12.3), Tables 6–7]. The tables include potentially significant interactions, but are not all inclusive.

Table 4 Established and Other Potentially Significant Drug Interactions: Alteration in Dose or Regimen May Be Recommended Based on Drug Interaction Studies or Predicted Interaction
Concomitant Drug Class: Drug Name | Effect on Concentration | Clinical Comment
Antacids: antacids (e.g., aluminium, magnesium hydroxide, or calcium carbonate) | ↔ rilpivirine (antacids taken at least 2 hours before or at least 4 hours after rilpivirine) ↓ rilpivirine (concomitant intake) | The combination of COMPLERA and antacids should be used with caution as coadministration may cause significant decreases in rilpivirine plasma concentrations (increase in gastric pH). Antacids should only be administered either at least 2 hours before or at least 4 hours after COMPLERA.
Azole Antifungal Agents: fluconazole itraconazole ketoconazole posaconazole voriconazole | ↑ rilpivirine [The interaction was evaluated in a clinical study. All other drug-drug interactions shown are predicted.] , [This interaction study has been performed with a dose higher than the recommended dose for rilpivirine. The dosing recommendation is applicable to the recommended dose of rilpivirine 25 mg once daily.] ↓ ketoconazole, | Concomitant use of COMPLERA with azole antifungal agents may cause an increase in the plasma concentrations of rilpivirine (inhibition of CYP3A enzymes). No dose adjustment is required when COMPLERA is coadministered with azole antifungal agents. Clinically monitor for breakthrough fungal infections when azole antifungals are coadministered with COMPLERA.
H2-Receptor Antagonists: cimetidine famotidine nizatidine ranitidine | ↔ rilpivirine, (famotidine taken 12 hours before rilpivirine or 4 hours after rilpivirine) ↓ rilpivirine, (famotidine taken 2 hours before rilpivirine) | The combination of COMPLERA and H2-receptor antagonists should be used with caution as coadministration may cause significant decreases in rilpivirine plasma concentrations (increase in gastric pH). H2-receptor antagonists should only be administered at least 12 hours before or at least 4 hours after COMPLERA.
Macrolide or Ketolide Antibiotics: clarithromycin erythromycin telithromycin | ↑ rilpivirine ↔ clarithromycin ↔ erythromycin ↔ telithromycin | Concomitant use of COMPLERA with clarithromycin, erythromycin or telithromycin may cause an increase in the plasma concentrations of rilpivirine (inhibition of CYP3A enzymes). Where possible, alternatives such as azithromycin should be considered.
Narcotic Analgesics: methadone | ↓ R(–) methadone ↓ S(+) methadone ↔ rilpivirine ↔ methadone (when used with tenofovir) | No dose adjustments are required when initiating coadministration of methadone with COMPLERA. However, clinical monitoring is recommended as methadone maintenance therapy may need to be adjusted in some patients.

7.6 Drugs with No Observed or Predicted Interactions with COMPLERA

No clinically significant drug interactions have been observed between emtricitabine and the following medications: famciclovir or tenofovir DF. Similarly, no clinically significant drug interactions have been observed between tenofovir DF and the following medications: entecavir, methadone, oral contraceptives, ribavirin, or tacrolimus in studies conducted in healthy subjects.

No clinically significant drug interactions have been observed between rilpivirine and the following medications: acetaminophen, atorvastatin, chlorzoxazone, ethinyl estradiol, norethindrone, sildenafil, or tenofovir DF. No clinically relevant drug-drug interaction is expected when rilpivirine is coadministered with ribavirin.

8 USE IN SPECIFIC POPULATIONS

8.1 Pregnancy

TERATOGENIC EFFECTS

Pregnancy Category B

Emtricitabine: The incidence of fetal variations and malformations was not increased in embryofetal toxicity studies performed with emtricitabine in mice at exposures (AUC) approximately 60 times higher and in rabbits at approximately 120-times higher than human exposures at the recommended daily dose.

Rilpivirine: Studies in animals have shown no evidence of embryonic or fetal toxicity or an effect on reproductive function. In offspring from rat and rabbit dams treated with rilpivirine during pregnancy and lactation, there were no toxicologically significant effects on developmental endpoints. The exposures at the embryo-fetal No Observed Adverse Effects Levels in rats and rabbits were respectively 15 and 70 times higher than the exposure in humans at the recommended dose of 25 mg once daily.

Tenofovir Disoproxil Fumarate: Reproduction studies have been performed in rats and rabbits at doses up to 14 and 19 times the human dose based on body surface area comparisons and revealed no evidence of impaired fertility or harm to the fetus due to tenofovir.

There are, however, no adequate and well-controlled studies in pregnant women. Because animal reproduction studies are not always predictive of human response, COMPLERA should be used during pregnancy only if the potential benefit justifies the potential risk to the fetus.

Antiretroviral Pregnancy Registry: To monitor fetal outcomes of pregnant women exposed to COMPLERA, an Antiretroviral Pregnancy Registry has been established. Healthcare providers are encouraged to register patients by calling 1-800-258-4263.

8.3 Nursing Mothers

The Centers for Disease Control and Prevention recommend that HIV infected mothers not breastfeed their infants to avoid risking postnatal transmission of HIV.

Emtricitabine: Samples of breast milk obtained from five HIV-1 infected mothers show that emtricitabine is secreted in human milk. Breastfeeding infants whose mothers are being treated with emtricitabine may be at risk for developing viral resistance to emtricitabine. Other emtricitabine-associated risks in infants breastfed by mothers being treated with emtricitabine are unknown.

Rilpivirine: Studies in lactating rats and their offspring indicate that rilpivirine was present in rat milk. It is not known whether rilpivirine is secreted in human milk.

Tenofovir Disoproxil Fumarate: Samples of breast milk obtained from five HIV-1 infected mothers in the first post-partum week show that tenofovir is excreted in human milk. The impact of this exposure in breastfed infants is unknown.

Because of both the potential for HIV transmission and the potential for serious adverse reactions in nursing infants, mothers should be instructed not to breastfeed if they are receiving COMPLERA.

8.4 Pediatric Use

COMPLERA is not recommended for patients less than 18 years of age because not all the individual components of the COMPLERA have safety, efficacy and dosing recommendations available for all pediatric age groups [See Clinical Pharmacology (12.3)].

8.5 Geriatric Use

Clinical studies of emtricitabine, rilpivirine, or tenofovir DF did not include sufficient numbers of subjects aged 65 and over to determine whether they respond differently from younger subjects. In general, dose selection for the elderly patients should be cautious, keeping in mind the greater frequency of decreased hepatic, renal, or cardiac function, and of concomitant disease or other drug therapy [See Clinical Pharmacology (12.3)].

8.6 Renal Impairment

Because COMPLERA is a fixed-dose combination, it should not be prescribed for patients requiring dosage adjustment such as those with moderate, severe or end stage renal impairment (creatinine clearance below 50 mL per minute) or that require dialysis [See Warnings and Precautions (5.3), Clinical Pharmacology (12.3)].

8.7 Hepatic Impairment

No dose adjustment of COMPLERA is required in patients with mild (Child-Pugh Class A) or moderate (Child-Pugh Class B) hepatic impairment. COMPLERA has not been studied in patients with severe hepatic impairment (Child-Pugh Class C) [See Clinical Pharmacology (12.3)].

10 OVERDOSAGE

If overdose occurs the patient must be monitored for evidence of toxicity. Treatment of overdose with COMPLERA consists of general supportive measures including monitoring of vital signs and ECG (QT interval) as well as observation of the clinical status of the patient.

Emtricitabine: Limited clinical experience is available at doses higher than the therapeutic dose of EMTRIVA. In one clinical pharmacology study, single doses of emtricitabine 1200 mg were administered to 11 subjects. No severe adverse reactions were reported. The effects of higher doses are not known.

Hemodialysis treatment removes approximately 30% of the emtricitabine dose over a 3-hour dialysis period starting within 1.5 hours of emtricitabine dosing (blood flow rate of 400 mL per minute and a dialysate flow rate of 600 mL per minute). It is not known whether emtricitabine can be removed by peritoneal dialysis.

Rilpivirine: There is no specific antidote for overdose with rilpivirine. Human experience of overdose with rilpivirine is limited. Since rilpivirine is highly bound to plasma protein, dialysis is unlikely to result in significant removal of rilpivirine.

If indicated, elimination of unabsorbed active substance may be achieved by gastric lavage. Administration of activated charcoal may also be used to aid in removal of unabsorbed active substance.

Tenofovir Disoproxil Fumarate: Limited clinical experience at doses higher than the therapeutic dose of VIREAD 300 mg is available. In one study, 600 mg tenofovir DF was administered to 8 subjects orally for 28 days, and no severe adverse reactions were reported. The effects of higher doses are not known.

Tenofovir is efficiently removed by hemodialysis with an extraction coefficient of approximately 54%. Following a single 300 mg dose of VIREAD, a four-hour hemodialysis session removed approximately 10% of the administered tenofovir dose.

11 DESCRIPTION

COMPLERA is a fixed-dose combination tablet containing emtricitabine, rilpivirine hydrochloride, and tenofovir DF. EMTRIVA is the brand name for emtricitabine, a synthetic nucleoside analog of cytidine. EDURANT is the brand name for rilpivirine, a non-nucleoside reverse transcriptase inhibitor. VIREAD is the brand name for tenofovir DF, which is converted in vivo to tenofovir, an acyclic nucleoside phosphonate (nucleotide) analog of adenosine 5′-monophosphate. VIREAD and EMTRIVA are the components of TRUVADA.

COMPLERA tablets are for oral administration. Each tablet contains 200 mg of emtricitabine, 27.5 mg of rilpivirine hydrochloride (equivalent to 25 mg of rilpivirine), and 300 mg of tenofovir DF (equivalent to 245 mg of tenofovir disoproxil) as active ingredients. The tablets include the following inactive ingredients: pregelatinized starch, lactose monohydrate, microcrystalline cellulose, croscarmellose sodium, magnesium stearate, povidone, polysorbate 20. The tablets are film-coated with a coating material containing polyethylene glycol, hypromellose, lactose monohydrate, triacetin, titanium dioxide, iron oxide red, FD&C Blue #2 aluminum lake, FD&C Yellow #6 aluminum lake.

Emtricitabine: The chemical name of emtricitabine is 5-fluoro-1-[(2R,5S)-2-(hydroxymethyl)-1,3-oxathiolan-5-yl]cytosine. Emtricitabine is the (–) enantiomer of a thio analog of cytidine, which differs from other cytidine analogs in that it has a fluorine in the 5-position.

It has a molecular formula of C8H10FN3O3S and a molecular weight of 247.24. It has the following structural formula:

Emtricitabine is a white to off-white crystalline powder with a solubility of approximately 112 mg per mL in water at 25 °C.

Rilpivirine: Rilpivirine is available as the hydrochloride salt. The chemical name for rilpivirine hydrochloride is 4-[[4-[[4-[(E)-2-cyanoethenyl]-2,6-dimethylphenyl]amino]-2-pyrimidinyl]amino]benzonitrile monohydrochloride. Its molecular formula is C22H18N6 • HCl and its molecular weight is 402.88. Rilpivirine hydrochloride has the following structural formula:

Rilpivirine hydrochloride is a white to almost white powder. Rilpivirine hydrochloride is practically insoluble in water over a wide pH range.

Tenofovir Disoproxil Fumarate: Tenofovir DF is a fumaric acid salt of the bis-isopropoxycarbonyloxymethyl ester derivative of tenofovir. The chemical name of tenofovir DF is 9-[(R)-2 [[bis[[(isopropoxycarbonyl)oxy]- methoxy]phosphinyl]methoxy]propyl]adenine fumarate (1:1). It has a molecular formula of C19H30N5O10P • C4H4O4 and a molecular weight of 635.52. It has the following structural formula:

Tenofovir DF is a white to off-white crystalline powder with a solubility of 13.4 mg per mL in water at 25 °C. All dosages are expressed in terms of tenofovir DF except where otherwise noted.

12 CLINICAL PHARMACOLOGY

12.1 Mechanism of Action

COMPLERA is a fixed-dose combination of antiviral drugs emtricitabine, rilpivirine and tenofovir disoproxil fumarate [See Microbiology (12.4)].

12.2 Pharmacodynamics

Effects on Electrocardiogram

The effect of rilpivirine at the recommended dose of 25 mg once daily on the QTcF interval was evaluated in a randomized, placebo and active (moxifloxacin 400 mg once daily) controlled crossover study in 60 healthy adults, with 13 measurements over 24 hours at steady state. The maximum mean time-matched (95% upper confidence bound) differences in QTcF interval from placebo after baseline-correction was 2.0 (5.0) milliseconds (i.e., below the threshold of clinical concern).

When supratherapeutic doses of 75 mg once daily and 300 mg once daily of rilpivirine were studied in healthy adults, the maximum mean time-matched (95% upper confidence bound) differences in QTcF interval from placebo after baseline-correction were 10.7 (15.3) and 23.3 (28.4) milliseconds, respectively. Steady-state administration of rilpivirine 75 mg once daily and 300 mg once daily resulted in a mean steady-state Cmax approximately 2.6-fold and 6.7-fold, respectively, higher than the mean Cmax observed with the recommended 25 mg once daily dose of rilpivirine [See Warnings and Precautions (5.4)].

12.3 Pharmacokinetics

COMPLERA: Under fed conditions (total calorie content of the meal was approximately 400 kcal with approximately 13 grams of fat), rilpivirine, emtricitabine and tenofovir exposures were bioequivalent when comparing COMPLERA to EMTRIVA capsules (200 mg) plus EDURANT tablets (25 mg) plus VIREAD tablets (300 mg) following single-dose administration to healthy subjects (N=34).

Single-dose administration of COMPLERA tablet to healthy subjects under fasted conditions provided approximately 25% higher exposure of rilpivirine compared to administration of EMTRIVA capsules (200 mg) plus EDURANT tablets (25 mg) plus VIREAD tablets (300 mg), while exposures of emtricitabine and tenofovir were comparable (N=15).

Emtricitabine: Following oral administration, emtricitabine is absorbed with peak plasma concentrations occurring at 1–2 hours post-dose. Following multiple dose oral administration of EMTRIVA to 20 HIV-1 infected subjects, the mean steady-state plasma emtricitabine Cmax was 1.8 ± 0.7 µg per mL and the AUC over a 24-hour dosing interval was 10.0 ± 3.1 µg∙hr per mL. The mean steady state plasma trough concentration at 24 hours post-dose was 0.09 µg per mL. The mean absolute bioavailability of EMTRIVA capsules was 93%. Less than 4% of emtricitabine binds to human plasma proteins in vitro over the range of 0.02 to 200 µg per mL. Following administration of radiolabelled emtricitabine, approximately 86% is recovered in the urine, approximately 14% in the feces and 13% is recovered as metabolites in the urine. The metabolites of emtricitabine include 3′-sulfoxide diastereomers (approximately 9% of the dose) and the glucuronic acid conjugate (approximately 4% of the dose). Emtricitabine is eliminated by a combination of glomerular filtration and active tubular secretion with a renal clearance in adults with creatinine clearance >80 mL per minute of 213 ± 89 mL per minute (mean ± SD). The plasma emtricitabine half-life is approximately 10 hours.

Rilpivirine: The pharmacokinetic properties of rilpivirine have been evaluated in adult healthy subjects and in adult antiretroviral treatment-naive HIV-1 infected subjects. Exposure to rilpivirine was generally lower in HIV-1 infected subjects than in healthy subjects. After oral administration, the Cmax of rilpivirine is achieved within 4–5 hours. The absolute bioavailability of rilpivirine is unknown.

Table 5 Population Pharmacokinetic Estimates of Rilpivirine 25 mg Once Daily in Antiretroviral Treatment-Naive HIV-1-infected Subjects (Pooled Data from Phase 3 Trials through Week 96)
Parameter | Rilpivirine 25 mg once daily N=679
AUC24h (ng∙h/mL)
Mean ± Standard Deviation | 2235 ± 851
Median (Range) | 2096 (198 – 7307)
C0h (ng/mL)
Mean ± Standard Deviation | 79 ± 35
Median (Range) | 73 (2 – 288)

Rilpivirine is approximately 99.7% bound to plasma proteins in vitro, primarily to albumin. In vitro experiments indicate that rilpivirine primarily undergoes oxidative metabolism by the cytochrome CYP3A system. The terminal elimination half-life of rilpivirine is approximately 50 hours. After single dose oral administration of ^14C-rilpivirine, on average 85% and 6.1% of the radioactivity could be retrieved in feces and urine, respectively. In feces, unchanged rilpivirine accounted for on average 25% of the administered dose. Only trace amounts of unchanged rilpivirine (less than 1% of dose) were detected in urine.

Tenofovir Disoproxil Fumarate: Following oral administration of a single 300 mg dose of VIREAD to HIV-1 infected subjects in the fasted state, Cmax was achieved in one hour. Cmax and AUC values were 0.30 ± 0.09 µg per mL and 2.29 ± 0.69 µg∙hr per mL, respectively. The oral bioavailability of tenofovir from VIREAD in fasted subjects is approximately 25%. Less than 0.7% of tenofovir binds to human plasma proteins in vitro over the range of 0.01 to 25 µg per mL. Approximately 70–80% of the intravenous dose of tenofovir is recovered as unchanged drug in the urine within 72 hours of dosing. Tenofovir is eliminated by a combination of glomerular filtration and active tubular secretion with a renal clearance in adults with creatinine clearance >80 mL per minute of 243.5 ± 33.3 mL per minute (mean ± SD). Following a single oral dose, the terminal elimination half-life of tenofovir is approximately 17 hours.

Effects of Food on Oral Absorption

Take COMPLERA with a meal. A food effect trial was not conducted for COMPLERA. Therefore, the specific effect of food with COMPLERA tablets on rilpivirine, emtricitabine and tenofovir exposure has not been established. The recommendation to administer COMPLERA with a meal is based on the increased exposure that was observed when rilpivirine tablets were administered under fed conditions.

Special Populations

Race

Emtricitabine: No pharmacokinetic differences due to race have been identified following the administration of EMTRIVA.

Rilpivirine: Population pharmacokinetic analysis of rilpivirine in HIV-1 infected subjects indicated that race had no clinically relevant effect on the exposure to rilpivirine.

Tenofovir Disoproxil Fumarate: There were insufficient numbers from racial and ethnic groups other than Caucasian to adequately determine potential pharmacokinetic differences among these populations following the administration of VIREAD.

Gender

No clinically relevant pharmacokinetic differences have been observed between men and women for emtricitabine, rilpivirine, and tenofovir DF.

Pediatric Patients

Emtricitabine has been studied in pediatric subjects from 3 months to 17 years of age. Tenofovir DF has been studied in adolescent subjects (12 to less than 18 years of age). The pharmacokinetics of rilpivirine in pediatric subjects have not been established.

Geriatric Patients

Pharmacokinetics of emtricitabine, rilpivirine and tenofovir have not been fully evaluated in the elderly (65 years of age and older) [See Use in Specific Populations (8.5)].

Patients with Renal Impairment

Emtricitabine and Tenofovir Disoproxil Fumarate: The pharmacokinetics of emtricitabine and tenofovir DF are altered in subjects with renal impairment. In subjects with creatinine clearance below 50 mL per minute or with end stage renal disease requiring dialysis, Cmax, and AUC of emtricitabine and tenofovir were increased [See Warnings and Precautions (5.3) and Use in Specific Populations (8.6)].

Rilpivirine: Population pharmacokinetic analysis indicated that rilpivirine exposure was similar in HIV-1 infected subjects with mild renal impairment relative to HIV-1 infected subjects with normal renal function. There is limited or no information regarding the pharmacokinetics of rilpivirine in patients with moderate or severe renal impairment or in patients with end-stage renal disease, and rilpivirine concentrations may be increased due to alteration of drug absorption, distribution, and metabolism secondary to renal dysfunction [See Use in Specific Populations (8.6)].

Patients with Hepatic Impairment

Emtricitabine: The pharmacokinetics of emtricitabine have not been studied in subjects with hepatic impairment; however, emtricitabine is not significantly metabolized by liver enzymes, so the impact of liver impairment should be limited.

Rilpivirine: Rilpivirine is primarily metabolized and eliminated by the liver. In a study comparing 8 subjects with mild hepatic impairment (Child-Pugh score A) to 8 matched controls and 8 subjects with moderate hepatic impairment (Child-Pugh score B) to 8 matched controls, the multiple dose exposure of rilpivirine was 47% higher in subjects with mild hepatic impairment and 5% higher in subjects with moderate hepatic impairment [See Use in Specific Populations (8.7)].

Tenofovir Disoproxil Fumarate: The pharmacokinetics of tenofovir following a 300 mg dose of VIREAD have been studied in non-HIV infected subjects with moderate to severe hepatic impairment. There were no substantial alterations in tenofovir pharmacokinetics in subjects with hepatic impairment compared with unimpaired subjects.

Hepatitis B and/or Hepatitis C Virus Coinfection

Pharmacokinetics of emtricitabine and tenofovir DF have not been fully evaluated in hepatitis B and/or C virus-coinfected patients. Population pharmacokinetic analysis indicated that hepatitis B and/or C virus coinfection had no clinically relevant effect on the exposure to rilpivirine.

Assessment of Drug Interactions

COMPLERA is a complete regimen for the treatment of HIV-1 infection; therefore, COMPLERA should not be administered with other antiretroviral medications. Information regarding potential drug-drug interactions with other antiretroviral medications is not provided. Please refer to the EDURANT, VIREAD and EMTRIVA prescribing information as needed.

The drug interaction studies described were conducted with emtricitabine, rilpivirine, or tenofovir DF as individual agents; no drug interaction studies have been conducted using COMPLERA.

Emtricitabine and Tenofovir Disoproxil Fumarate: In vitro and clinical pharmacokinetic drug-drug interaction studies have shown that the potential for CYP mediated interactions involving emtricitabine and tenofovir with other medicinal products is low.

Emtricitabine and tenofovir are primarily excreted by the kidneys by a combination of glomerular filtration and active tubular secretion. No drug-drug interactions due to competition for renal excretion have been observed; however, coadministration of emtricitabine and tenofovir DF with drugs that are eliminated by active tubular secretion may increase concentrations of emtricitabine, tenofovir, and/or the coadministered drug [See Drug Interactions (7.6)].

Drugs that decrease renal function may increase concentrations of emtricitabine and/or tenofovir.

Drug interaction studies were performed for emtricitabine and the following medications: tenofovir DF and famciclovir. Tenofovir increased the Cmin of emtricitabine by 20% (90% confidence interval [CI]: [↑12 to ↑29]) and had no effect on emtricitabine Cmax and AUC. Emtricitabine had no effect on the Cmax, AUC and Cmin of tenofovir. Coadministration of emtricitabine and famciclovir had no effect on the Cmax or AUC of either medication.

Drug interaction studies were performed for tenofovir DF and the following medications: entecavir, methadone, oral contraceptives (ethinyl estradiol/norgestimate), ribavirin, and tacrolimus. Tacrolimus increased the Cmax of tenofovir by 13% (90% CI: [↑1 to ↑27]) and had no effect on the tenofovir AUC and Cmin. Tenofovir had no effect on the Cmax, AUC and Cmin of tacrolimus.

The Cmax, AUC and Cmin of tenofovir were not affected in the presence of entecavir. Tenofovir increased the AUC of entecavir by 13% (90% CI: [↑11 to ↑15]) and had no effect on the entecavir Cmax and Cmin.

Tenofovir had no effect on the Cmax, AUC and Cmin of methadone or ethinyl estradiol/norgestimate or the Cmax and AUC of ribavirin.

Rilpivirine: Rilpivirine is primarily metabolized by cytochrome CYP3A, and drugs that induce or inhibit CYP3A may thus affect the clearance of rilpivirine. Coadministration of COMPLERA and drugs that induce CYP3A may result in decreased plasma concentrations of rilpivirine and loss of virologic response and possible resistance. Coadministration of COMPLERA and drugs that inhibit CYP3A may result in increased plasma concentrations of rilpivirine. Coadministration of COMPLERA with drugs that increase gastric pH may result in decreased plasma concentrations of rilpivirine and loss of virologic response and possible resistance to rilpivirine and to the class of NNRTIs.

Rilpivirine at a dose of 25 mg once daily is not likely to have a clinically relevant effect on the exposure of medicinal products metabolized by CYP enzymes.

The effects of coadministration of other drugs on the AUC, Cmax and Cmin values of rilpivirine are summarized in Table 6. The effect of coadministration of rilpivirine on the AUC, Cmax and Cmin values of other drugs are summarized in Table 7. For information regarding clinical recommendations, see Drug Interactions (7).

Table 6 Drug Interactions: Changes in Pharmacokinetic Parameters for Rilpivirine in the Presence of the Coadministered Drugs
Coadministered Drug | Dose of Coadministered Drug (mg) | Dose of Rilpivirine | N | Mean % Change of Rilpivirine Pharmacokinetic Parameters (90% CI)
Coadministered Drug | Dose of Coadministered Drug (mg) | Dose of Rilpivirine | N | Cmax | AUC | Cmin
Acetaminophen | 500 mg single dose | 150 mg once daily [The Interaction study has been performed with a dose higher than the recommended dose for rilpivirine (25 mg once daily) assessing the maximal effect on the coadministered drug.] | 16 | ↑ 9 (↑ 1 to ↑ 18) | ↑ 16 (↑ 10 to ↑ 22) | ↑ 26 (↑ 16 to ↑ 38)
Atorvastatin | 40 mg once daily | 150 mg once daily | 16 | ↓ 9 (↓ 21 to↑ 6) | ↓ 10 (↓ 19 to ↓ 1) | ↓ 10 (↓ 16 to ↓ 4)
Chlorzoxazone | 500 mg single dose | 150 mg once daily | 16 | ↑ 17 (↑ 8 to ↑ 27) | ↑ 25 (↑ 16 to ↑ 35) | ↑ 18 (↑ 9 to ↑ 28)
Ethinyl estradiol/ Norethindrone | 0.035 mg once daily/1 mg once daily | 25 mg once daily | 16 | ↔ | ↔ | ↔
Famotidine | 40 mg single dose taken 12 hours before rilpivirine | 150 mg single dose | 24 | ↓ 1 (↓ 16 to↑ 16) | ↓ 9 (↓ 22 to↑ 7) | NA
Famotidine | 40 mg single dose taken 2 hours before rilpivirine | 150 mg single dose | 23 | ↓ 85 (↓ 88 to ↓ 81) | ↓ 76 (↓ 80 to ↓ 72) | NA
Famotidine | 40 mg single dose taken 4 hours after rilpivirine | 150 mg single dose | 24 | ↑ 21 (↑ 6 to↑ 39) | ↑ 13 (↑ 1 to↑ 27) | NA
Ketoconazole | 400 mg once daily | 150 mg once daily | 15 | ↑ 30 (↑ 13 to ↑ 48) | ↑ 49 (↑ 31 to ↑ 70) | ↑ 76 (↑ 57 to ↑ 97)
Methadone | 60 –100 mg once daily individualized dose | 25 mg once daily | 12 | ↔ [Comparison based on historic controls.] | ↔ | ↔
Omeprazole | 20 mg once daily | 150 mg once daily | 16 | ↓ 40 (↓ 52 to ↓ 27) | ↓ 40 (↓ 49 to ↓ 29) | ↓ 33 (↓ 42 to ↓ 22)
Rifabutin | 300 mg once daily | 150 mg once daily | 16 | ↓ 35 (↓ 42 to ↓ 26) | ↓ 46 (↓ 50 to ↓ 42) | ↓ 49 (↓ 52 to ↓ 46)
Rifampin | 600 mg once daily | 150 mg once daily | 16 | ↓ 69 (↓ 73 to ↓ 64) | ↓ 80 (↓ 82 to ↓ 77) | ↓ 89 (↓ 90 to ↓ 87)
Sildenafil | 50 mg single dose | 75 mg once daily | 16 | ↓ 8 (↓ 15 to ↓ 1) | ↓ 2 (↓ 8 to ↑ 5) | ↑ 4 (↓ 2 to ↑ 9)
NA = not available

Table 7 Drug Interactions: Changes in Pharmacokinetic Parameters for Coadministered Drug in the Presence of Rilpivirine
Coadministered Drug | Dose of Coadministered Drug (mg) | Dose of Rilpivirine | N | Mean % Change of Coadministered Drug Pharmacokinetic Parameters (90% CI)
Coadministered Drug | Dose of Coadministered Drug (mg) | Dose of Rilpivirine | N | Cmax | AUC | Cmin
Acetaminophen | 500 mg single dose | 150 mg once daily [The Interaction study has been performed with a dose higher than the recommended dose for rilpivirine (25 mg once daily).] | 16 | ↓ 3 (↓ 14 to ↑ 10) | ↓ 8 (↓ 15 to ↓ 1) | NA
Atorvastatin | 40 mg once daily | 150 mg once daily | 16 | ↑ 35 (↑ 8 to ↑ 68) | ↑ 4 (↓ 3 to ↑ 12) | ↓ 15 (↓ 31 to ↑ 3)
2-hydroxy-atorvastatin | 40 mg once daily | 150 mg once daily | 16 | ↑ 58 (↑ 33 to ↑ 87) | ↑ 39 (↑ 29 to ↑ 50) | ↑ 32 (↑ 10 to ↑ 58)
4-hydroxy-atorvastatin | 40 mg once daily | 150 mg once daily | 16 | ↑ 28 (↑ 15 to ↑ 43) | ↑ 23 (↑ 13 to ↑ 33) | NA
Chlorzoxazone | 500 mg single dose | 150 mg once daily | 16 | ↓ 2 (↓ 15 to ↑ 13) | ↑ 3 (↓ 5 to ↑ 13) | NA
Ethinyl estradiol | 0.035 mg once daily | 25 mg once daily | 17 | ↑ 17 (↑ 6 to ↑ 30) | ↑ 14 (↑ 10 to ↑ 19) | ↑ 9 (↑ 3 to ↑ 16)
Norethindrone | 1 mg once daily | 25 mg once daily | 17 | ↓ 6 (↓ 17 to ↑ 6) | ↓ 11 (↓ 16 to ↓ 6) | ↓ 1 (↓ 10 to ↑ 8)
Ketoconazole | 400 mg once daily | 150 mg once daily | 14 | ↓ 15 (↓ 20 to ↓ 10) | ↓ 24 (↓ 30 to ↓ 18) | ↓ 66 (↓ 75 to ↓ 54)
R(–) methadone | 60–100 mg once daily individualized dose | 25 mg once daily | 13 | ↓ 14 (↓ 22 to ↓ 5) | ↓ 16 (↓ 26 to ↓ 5) | ↓ 22 (↓ 33 to ↓ 9)
S(+) methadone | 60–100 mg once daily individualized dose | 25 mg once daily | 13 | ↓ 13 (↓ 22 to ↓ 3) | ↓ 16 (↓ 26 to ↓ 4) | ↓ 21 (↓ 33 to ↓ 8)
Omeprazole | 20 mg once daily | 150 mg once daily | 15 | ↓ 14 (↓ 32 to ↑ 9) | ↓ 14 (↓ 24 to ↓ 3) | NA
Rifampin | 600 mg once daily | 150 mg once daily | 16 | ↑ 2 (↓ 7 to ↑ 12) | ↓ 1 (↓ 8 to ↑ 7) | NA
25-desacetylrifampin | 600 mg once daily | 150 mg once daily | 16 | ↔ (↓ 13 to ↑ 15) | ↓ 9 (↓ 23 to ↑ 7) | NA
Sildenafil | 50 mg single dose | 75 mg once daily | 16 | ↓ 7 (↓ 20 to ↑ 8) | ↓ 3 (↓ 13 to ↑ 8) | NA
N-desmethyl-sildenafil | 50 mg single dose | 75 mg once daily | 16 | ↓ 10 (↓ 20 to ↑ 2) | ↓ 8 (↓ 15 to↓ 1) | NA
NA = not available

12.4 Microbiology

Mechanism of Action

Emtricitabine: Emtricitabine, a synthetic nucleoside analog of cytidine, is phosphorylated by cellular enzymes to form emtricitabine 5'-triphosphate. Emtricitabine 5'-triphosphate inhibits the activity of the HIV-1 RT by competing with the natural substrate deoxycytidine 5'-triphosphate and by being incorporated into nascent viral DNA which results in chain termination. Emtricitabine 5′-triphosphate is a weak inhibitor of mammalian DNA polymerase α, β, ε, and mitochondrial DNA polymerase γ.

Rilpivirine: Rilpivirine is a diarylpyrimidine non-nucleoside reverse transcriptase inhibitor of HIV-1 and inhibits HIV-1 replication by non-competitive inhibition of HIV-1 RT. Rilpivirine does not inhibit the human cellular DNA polymerases α, β, and mitochondrial DNA polymerase γ.

Tenofovir Disoproxil Fumarate: Tenofovir DF is an acyclic nucleoside phosphonate diester analog of adenosine monophosphate. Tenofovir DF requires initial diester hydrolysis for conversion to tenofovir and subsequent phosphorylations by cellular enzymes to form tenofovir diphosphate. Tenofovir diphosphate inhibits the activity of HIV-1 RT by competing with the natural substrate deoxyadenosine 5′-triphosphate and, after incorporation into DNA, by DNA chain termination. Tenofovir diphosphate is a weak inhibitor of mammalian DNA polymerases α, β, and mitochondrial DNA polymerase γ.

Antiviral Activity

Emtricitabine, Rilpivirine, and Tenofovir Disoproxil Fumarate: The triple combination of emtricitabine, rilpivirine, and tenofovir was not antagonistic in cell culture.

Emtricitabine: The antiviral activity of emtricitabine against laboratory and clinical isolates of HIV-1 was assessed in lymphoblastoid cell lines, the MAGI-CCR5 cell line, and peripheral blood mononuclear cells. The 50% effective concentration (EC50) values for emtricitabine were in the range of 0.0013–0.64 µM. Emtricitabine displayed antiviral activity in cell culture against HIV-1 clades A, B, C, D, E, F, and G (EC50 values ranged from 0.007–0.075 µM) and showed strain specific activity against HIV-2 (EC50 values ranged from 0.007–1.5 µM). In drug combination studies of emtricitabine with nucleoside reverse transcriptase inhibitors (abacavir, lamivudine, stavudine, tenofovir, zidovudine), non-nucleoside reverse transcriptase inhibitors (delavirdine, efavirenz, nevirapine, and rilpivirine), and protease inhibitors (amprenavir, nelfinavir, ritonavir, saquinavir), no antagonistic effects were observed.

Rilpivirine: Rilpivirine exhibited activity against laboratory strains of wild-type HIV-1 in an acutely infected T-cell line with a median EC50 value for HIV-1IIIB of 0.73 nM. Rilpivirine demonstrated limited activity in cell culture against HIV-2 with a median EC50 value of 5220 nM (range 2510 to 10830 nM). Rilpivirine demonstrated antiviral activity against a broad panel of HIV-1 group M (subtype A, B, C, D, F, G, H) primary isolates with EC50 values ranging from 0.07 to 1.01 nM and was less active against group O primary isolates with EC50 values ranging from 2.88 to 8.45 nM. The antiviral activity of rilpivirine was not antagonistic when combined with the NNRTIs efavirenz, etravirine or nevirapine; N(t)RTIs abacavir, didanosine, emtricitabine, lamivudine, stavudine, tenofovir or zidovudine; the PIs amprenavir, atazanavir, darunavir, indinavir, lopinavir, nelfinavir, ritonavir, saquinavir or tipranavir; the fusion inhibitor enfuvirtide; the CCR5 co-receptor antagonist maraviroc or the integrase strand transfer inhibitor raltegravir.

Tenofovir Disoproxil Fumarate: The antiviral activity of tenofovir against laboratory and clinical isolates of HIV-1 was assessed in lymphoblastoid cell lines, primary monocyte/macrophage cells and peripheral blood lymphocytes. The EC50 values for tenofovir were in the range of 0.04–8.5 µM. Tenofovir displayed antiviral activity in cell culture against HIV-1 clades A, B, C, D, E, F, G, and O (EC50 values ranged from 0.5–2.2 µM) and showed strain specific activity against HIV-2 (EC50 values ranged from 1.6 µM–5.5 µM). In drug combination studies of tenofovir with NRTIs (abacavir, didanosine, emtricitabine, lamivudine, stavudine, and zidovudine), NNRTIs (delavirdine, efavirenz, nevirapine, and rilpivirine), and PIs (amprenavir, indinavir, nelfinavir, ritonavir, saquinavir), no antagonistic effects were observed.

Resistance

In Cell Culture

Emtricitabine and Tenofovir Disoproxil Fumarate: HIV-1 isolates with reduced susceptibility to emtricitabine or tenofovir have been selected in cell culture. Reduced susceptibility to emtricitabine was associated with M184V/I substitutions in HIV-1 RT. HIV-1 isolates selected by tenofovir expressed a K65R substitution in HIV-1 RT and showed a 2–4 fold reduction in susceptibility to tenofovir.

Rilpivirine: Rilpivirine-resistant strains were selected in cell culture starting from wild-type HIV-1 of different origins and subtypes as well as NNRTI resistant HIV-1. The frequently observed amino acid substitutions that emerged and conferred decreased phenotypic susceptibility to rilpivirine included: L100I, K101E, V106I and A, V108I, E138K and G, Q, R, V179F and I, Y181C and I, V189I, G190E, H221Y, F227C and M230I and L.

In Treatment-Naive HIV-1-infected Subjects

In the Week 96 pooled resistance analysis for subjects receiving rilpivirine or efavirenz in combination with emtricitabine/tenofovir DF in the Phase 3 clinical trials C209 and C215, the emergence of resistance was greater among subjects' viruses in the rilpivirine plus emtricitabine/tenofovir DF arm compared to the efavirenz plus emtricitabine/tenofovir DF arm and was dependent on baseline viral load. In the pooled resistance analysis, 61% (47/77) of the subjects who qualified for resistance analysis (resistance analysis subjects) in the rilpivirine plus emtricitabine/tenofovir DF arm had virus with genotypic and/or phenotypic resistance to rilpivirine compared to 42% (18/43) of the resistance analysis subjects in the efavirenz plus emtricitabine/tenofovir DF arm who had genotypic and/or phenotypic resistance to efavirenz. Moreover, genotypic and/or phenotypic resistance to emtricitabine or tenofovir emerged in viruses from 57% (44/77) of the resistance analysis subjects in the rilpivirine arm compared to 26% (11/43) in the efavirenz arm.

Emerging NNRTI substitutions in the rilpivirine resistance analysis of subjects' viruses included V90I, K101E/P/T, E138K/A/Q/G, V179I/L, Y181C/I, V189I, H221Y, F227C/L and M230L, which were associated with a rilpivirine phenotypic fold change range of 2.6–621. The E138K substitution emerged most frequently during rilpivirine treatment commonly in combination with the M184I substitution. The emtricitabine and lamivudine resistance-associated substitutions M184I or V and NRTI resistance-associated substitutions (K65R/N, A62V, D67N/G, K70E, Y115F, K219E/R) emerged more frequently in the rilpivirine resistance analysis subjects than in efavirenz resistance analysis subjects (See Table 8).

NNRTI- and NRTI-resistance substitutions emerged less frequently in the resistance analysis of viruses from subjects with baseline viral loads of ≤100,000 copies/mL compared to viruses from subjects with baseline viral loads of >100,000 copies/mL: 23% (10/44) compared to 77% (34/44) of NNRTI-resistance substitutions and 20% (9/44) compared to 80% (35/44) of NRTI-resistance substitutions. This difference was also observed for the individual emtricitabine/lamivudine and tenofovir resistance substitutions: 22% (9/41) compared to 78% (32/41) for M184I/V and 0% (0/8) compared to 100% (8/8) for K65R/N. Additionally, NNRTI and/or NRTI-resistance substitutions emerged less frequently in the resistance analysis of the viruses from subjects with baseline CD4+ cell counts ≥200 cells/mm^3 compared to the viruses from subjects with baseline CD4+ cell counts <200 cells/mm^3: 32% (14/44) compared to 68% (30/44) of NNRTI-resistance substitutions and 27% (12/44) compared to 73% (32/44) of NRTI-resistance substitutions.

Table 8 Proportion of Frequently Emerging Reverse Transcriptase Substitutions in the HIV-1 Virus of Resistance Analysis Subjects [Subjects who qualified for resistance analysis] Who Received Rilpivirine or Efavirenz in Combination with Emtricitabine/Tenofovir DF from Pooled Phase 3 TMC278-C209 and TMC278-C215 Trials in the Week 96 Analysis
 | C209 and C215 N=1096
 | Rilpivirine + FTC/TDF | Efavirenz + FTC/TDF
 | N=550 | N=546
Subjects who Qualified for Resistance Analysis | 14% (77/550) | 8% (43/546)
Subjects with Evaluable Post-Baseline Resistance Data | 70 | 31
Emergent NNRTI Substitutions [V90, L100, K101, K103, V106, V108, E138, V179, Y181, Y188, V189, G190, H221, P225, F227, and M230]
Any | 63% (44/70) | 55% (17/31)
V90I | 14% (10/70) | 0
K101E/P/T/Q | 19% (13/70) | 10% (3/31)
K103N | 1% (1/70) | 39% (12/31)
E138K/A/Q/G | 40% (28/70) | 0
E138K+M184I [This combination of NRTI and NNRTI substitutions is a subset of those with the E138K.] | 30% (21/70) | 0
V179I/D | 6% (4/70) | 10% (3/31)
Y181C/I/S | 13% (9/70) | 3% (1/31)
V189I | 9% (6/70) | 0
H221Y | 10% (7/70) | 0
Emergent NRTI Substitutions [A62V, K65R/N, D67N/G, K70E, L74I, Y115F, M184V/I, L210F, K219E/R]
Any | 63% (44/70) | 32% (10/31)
M184I/V | 59% (41/70) | 26% (8/31)
K65R/N | 11% (8/70) | 6% (2/31)
A62V, D67N/G, K70E, Y115F, or K219E/R [These substitutions emerged in addition to the primary substitutions M184V/I or K65R; A62V (n=2), D67N/G (n=3), K70E (n=4), Y115F (n=2), K219E/R (n=8) in rilpivirine resistance analysis subjects.] | 20% (14/70) | 3% (1/31)

Cross Resistance

Emtricitabine, Rilpivirine, and Tenofovir Disoproxil Fumarate:

In Cell Culture

No significant cross-resistance has been demonstrated between rilpivirine-resistant HIV-1 variants and emtricitabine or tenofovir, or between emtricitabine- or tenofovir-resistant variants and rilpivirine.

Rilpivirine:

Site-Directed NNRTI Mutant Virus

Cross-resistance has been observed among NNRTIs. The single NNRTI substitutions K101P, Y181I and Y181V conferred 52-fold, 15-fold and 12-fold decreased susceptibility to rilpivirine, respectively. The combination of E138K and M184I showed 6.7-fold reduced susceptibility to rilpivirine compared to 2.8-fold for E138K alone. The K103N substitution did not show reduced susceptibility to rilpivirine by itself. However, the combination of K103N and L100I resulted in a 7-fold reduced susceptibility to rilpivirine. In another study, the Y188L substitution resulted in a reduced susceptibility to rilpivirine of 9-fold for clinical isolates and 6-fold for site-directed mutants. Combinations of 2 or 3 NNRTI resistance-associated substitutions gave decreased susceptibility to rilpivirine (fold change range of 3.7–554) in 38% and 66% of mutants, respectively.

In Treatment-Naive HIV-1-infected Subjects

Considering all of the available cell culture and clinical data, any of the following amino acid substitutions, when present at baseline, are likely to decrease the antiviral activity of rilpivirine: K101E, K101P, E138A, E138G, E138K, E138R, E138Q, V179L, Y181C, Y181I, Y181V, Y188L, H221Y, F227C, M230I or M230L.

Cross-resistance to efavirenz, etravirine and/or nevirapine is likely after virologic failure and development of rilpivirine resistance. In a pooled 96-Week analysis for subjects receiving rilpivirine in combination with emtricitabine/tenofovir DF in the Phase 3 clinical trials TMC278-C209 and TMC278-C215, 43 of the 70 (61%) rilpivirine resistance analysis subjects with post-baseline resistance data had virus with decreased susceptibility to rilpivirine (≥2.5-fold). Of these, 84% (n=36/43) were resistant to efavirenz (≥3.3 fold change), 88% (n=38/43) were resistant to etravirine (≥3.2 fold change) and 60% (n=26/43) were resistant to nevirapine (≥6 fold change). In the efavirenz arm, 3 of the 15 (20%) efavirenz resistance analysis subjects had viruses with resistance to etravirine and rilpivirine, and 93% (14/15) had resistance to nevirapine. Virus from subjects experiencing virologic failure on rilpivirine in combination with emtricitabine/tenofovir DF developed more NNRTI resistance-associated substitutions conferring more cross-resistance to the NNRTI class and had a higher likelihood of cross-resistance to all NNRTIs in the class than subjects who failed on efavirenz.

Emtricitabine: Emtricitabine-resistant isolates (M184V/I) were cross-resistant to lamivudine but retained susceptibility in cell culture to didanosine, stavudine, tenofovir, zidovudine, and NNRTIs (delavirdine, efavirenz, nevirapine, and rilpivirine). HIV-1 isolates containing the K65R substitution, selected in vivo by abacavir, didanosine, and tenofovir, demonstrated reduced susceptibility to inhibition by emtricitabine. Viruses harboring substitutions conferring reduced susceptibility to stavudine and zidovudine (M41L, D67N, K70R, L210W, T215Y/F, K219Q/E), or didanosine (L74V) remained sensitive to emtricitabine. HIV-1 containing the substitutions associated with NNRTI resistance K103N or rilpivirine-associated substitutions were susceptible to emtricitabine.

Tenofovir Disoproxil Fumarate: The K65R substitution selected by tenofovir is also selected in some HIV-1 infected patients treated with abacavir or didanosine. HIV-1 isolates with the K65R substitution also showed reduced susceptibility to emtricitabine and lamivudine. Therefore, cross-resistance among these NRTIs may occur in patients whose virus harbors the K65R substitution. HIV-1 isolates from patients (N=20) whose HIV-1 expressed a mean of 3 zidovudine-associated RT amino acid substitutions (M41L, D67N, K70R, L210W, T215Y/F, or K219Q/E/N) showed a 3.1-fold decrease in the susceptibility to tenofovir.

Subjects whose virus expressed an L74V substitution without zidovudine resistance associated substitutions (N=8) had reduced response to VIREAD. Limited data are available for patients whose virus expressed a Y115F substitution (N=3), Q151M substitution (N=2), or T69 insertion (N=4), all of whom had a reduced response.

HIV-1 containing the substitutions associated with NNRTI resistance K103N and Y181C, or rilpivirine-associated substitutions were susceptible to tenofovir.

13 NONCLINICAL TOXICOLOGY

13.1 Carcinogenesis, Mutagenesis, Impairment of Fertility

Emtricitabine: In long-term carcinogenicity studies of emtricitabine, no drug-related increases in tumor incidence were found in mice at doses up to 750 mg per kg per day (26 times the human systemic exposure at the therapeutic dose of 200 mg per day) or in rats at doses up to 600 mg per kg per day (31 times the human systemic exposure at the therapeutic dose).

Emtricitabine was not genotoxic in the reverse mutation bacterial test (Ames test), mouse lymphoma or mouse micronucleus assays.

Emtricitabine did not affect fertility in male rats at approximately 140-fold or in male and female mice at approximately 60-fold higher exposures (AUC) than in humans given the recommended 200 mg daily dose. Fertility was normal in the offspring of mice exposed daily from before birth (in utero) through sexual maturity at daily exposures (AUC) of approximately 60-fold higher than human exposures at the recommended 200 mg daily dose.

Rilpivirine: Rilpivirine was evaluated for carcinogenic potential by oral gavage administration to mice and rats up to 104 weeks. Daily doses of 20, 60 and 160 mg per kg per day were administered to mice and doses of 40, 200, 500 and 1500 mg per kg per day were administered to rats. In rats, there were no drug related neoplasms. In mice, rilpivirine was positive for hepatocellular neoplasms in both males and females. The observed hepatocellular findings in mice may be rodent-specific. At the lowest tested doses in the carcinogenicity studies, the systemic exposures (based on AUC) to rilpivirine were 21 fold (mice) and 3 fold (rats), relative to those observed in humans at the recommended dose (25 mg once daily).

Rilpivirine has tested negative in the absence and presence of a metabolic activation system, in the in vitro Ames reverse mutation assay and in vitro clastogenicity mouse lymphoma assay. Rilpivirine did not induce chromosomal damage in the in vivo micronucleus test in mice.

In a study conducted in rats, there were no effects on mating or fertility with rilpivirine up to 400 mg per kg per day, a dose of rilpivirine that showed maternal toxicity. This dose is associated with an exposure that is approximately 40 times higher than the exposure in humans at the recommended dose of 25 mg once daily.

Tenofovir Disoproxil Fumarate: Long-term oral carcinogenicity studies of tenofovir DF in mice and rats were carried out at exposures up to approximately 16 times (mice) and 5 times (rats) those observed in humans at the therapeutic dose for HIV-1 infection. At the high dose in female mice, liver adenomas were increased at exposures 16 times that in humans. In rats, the study was negative for carcinogenic findings at exposures up to 5 times that observed in humans at the therapeutic dose.

Tenofovir DF was mutagenic in the in vitro mouse lymphoma assay and negative in an in vitro bacterial mutagenicity test (Ames test). In an in vivo mouse micronucleus assay, tenofovir DF was negative when administered to male mice.

There were no effects on fertility, mating performance or early embryonic development when tenofovir DF was administered to male rats at a dose equivalent to 10 times the human dose based on body surface area comparisons for 28 days prior to mating and to female rats for 15 days prior to mating through day seven of gestation. There was, however, an alteration of the estrous cycle in female rats.

13.2 Animal Toxicology and/or Pharmacology

Tenofovir Disoproxil Fumarate: Tenofovir and tenofovir DF administered in toxicology studies to rats, dogs and monkeys at exposures (based on AUCs) greater than or equal to 6-fold those observed in humans caused bone toxicity. In monkeys the bone toxicity was diagnosed as osteomalacia. Osteomalacia observed in monkeys appeared to be reversible upon dose reduction or discontinuation of tenofovir. In rats and dogs, the bone toxicity manifested as reduced bone mineral density. The mechanism(s) underlying bone toxicity is unknown.

Evidence of renal toxicity was noted in 4 animal species. Increases in serum creatinine, BUN, glycosuria, proteinuria, phosphaturia, and/or calciuria and decreases in serum phosphate were observed to varying degrees in these animals. These toxicities were noted at exposures (based on AUCs) 2–20 times higher than those observed in humans. The relationship of the renal abnormalities, particularly the phosphaturia, to the bone toxicity is not known.

14 CLINICAL STUDIES

The efficacy of COMPLERA is based on the analyses of 48- and 96-week data from two randomized, double-blind, controlled studies C209 (ECHO) and C215 (THRIVE) in treatment-naive, HIV-1 infected subjects (N=1368). The studies are identical in design with the exception of the background regimen (BR). Subjects were randomized in a 1:1 ratio to receive either rilpivirine 25 mg (N=686) once daily or efavirenz 600 mg (N=682) once daily in addition to a BR. In Study C209 (N=690), the BR was emtricitabine/tenofovir DF. In Study C215 (N=678), the BR consisted of 2 NRTIs: emtricitabine/tenofovir DF (60%, N=406) or lamivudine/zidovudine (30%, N=204) or abacavir plus lamivudine (10%, N=68).

For subjects who received emtricitabine/tenofovir DF (N=1096) in C209 and C215, the mean age was 37 years (range 18–78), 78% were male, 62% were White, 24% were Black, and 11% were Asian. The mean baseline CD4+ cell count was 265 cells/mm^3 (range 1–888) and 31% had CD4+ cell counts <200 cells/mm^3. The median baseline plasma HIV-1 RNA was 5 log10 copies/mL (range 2–7). Subjects were stratified by baseline HIV-1 RNA. Fifty percent of subjects had baseline viral loads ≤100,000 copies/mL, 39% of subjects had baseline viral load between 100,000 copies/mL to 500,000 copies/mL and 11% of subject had baseline viral load >500,000 copies/mL.

Treatment outcomes through 96 weeks for the subset of subjects receiving emtricitabine/tenofovir DF in studies C209 and C215 (Table 9) are generally consistent with treatment outcomes for all participating subjects (presented in the prescribing information for EDURANT). The incidence of virologic failure was higher in the rilpivirine arm than the efavirenz arm at Week 96. Virologic failures and discontinuations due to adverse events mostly occurred in the first 48 weeks of treatment.

Table 9 Virologic Outcome of Randomized Treatment of Studies C209 and C215 (Pooled Data for Subjects Receiving Rilpivirine or Efavirenz in Combination with Emtricitabine/Tenofovir DF) at Week 96 [Analyses were based on the last observed viral load data within the Week 96 window (Week 90–103).]
 | Rilpivirine + FTC/TDF | Efavirenz + FTC/TDF
 | N=550 | N=546
HIV-1 RNA <50 copies/mL [Predicted difference (95% CI) of response rate is 0.5% (-4.5% to 5.5%) at Week 96.] | 77% | 77%
HIV-1 RNA ≥50 copies/mL [Includes subjects who had ≥50 copies/mL in the Week 96 window, subjects who discontinued early due to lack or loss of efficacy, subjects who discontinued for reasons other than an adverse event, death or lack or loss of efficacy and at the time of discontinuation had a viral value of ≥50 copies/mL, and subjects who had a switch in background regimen that was not permitted by the protocol.] | 14% | 8%
No virologic data at Week 96 window Reasons
Discontinued study due to adverse event or death [Includes subjects who discontinued due to an adverse event or death if this resulted in no on-treatment virologic data in the Week 96 window.] | 4% | 9%
Discontinued study for other reasons [Includes subjects who discontinued for reasons other than an adverse event, death or lack or loss of efficacy, e.g., withdrew consent, loss to follow-up, etc.] and the last available HIV-1 RNA <50 copies/mL (or missing) | 4% | 6%
Missing data during window but on study | <1% | <1%
HIV-1 RNA <50 copies/mL by Baseline HIV-1 RNA (copies/mL)
≤100,000 | 83% | 80%
>100,000 | 71% | 74%
HIV-1 RNA ≥50 copies/mL by Baseline HIV-1 RNA (copies/mL)
≤100,000 | 7% | 5%
>100,000 | 22% | 12%
HIV-1 RNA <50 copies/mL by Baseline CD4+ Cell Count (cells/mm^3)
<200 | 68% | 72%
≥200 | 82% | 79%
HIV-1 RNA ≥50 copies/mL by Baseline CD4+ Cell Count (cells/mm^3)
<200 | 27% | 12%
≥200 | 8% | 7%

Based on the pooled data from studies C209 and C215, the mean CD4+ cell count increase from baseline at Week 96 was 226 cells/mm^3 for rilpivirine plus emtricitabine/tenofovir DF-treated subjects and 223 cells/mm^3 for efavirenz plus emtricitabine/tenofovir DF-treated subjects.

16 HOW SUPPLIED/STORAGE AND HANDLING

COMPLERA tablets are purplish-pink, capsule-shaped, film-coated, debossed with "GSI" on one side and plain-faced on the other side.

Each bottle contains 30 tablets (NDC 54868-6360-0), a silica gel desiccant, polyester fiber coil, and is closed with a child-resistant closure.

STORAGE AND HANDLING

Store at 25 °C (77 °F), excursions permitted to 15–30 °C (59–86 °F) (see USP Controlled Room Temperature).

- Keep container tightly closed
- Dispense only in original container
- Do not use if seal over bottle opening is broken or missing.

17 PATIENT COUNSELING INFORMATION

See FDA-Approved Patient Labeling (Patient Information)

A statement to patients and healthcare providers is included on the product's bottle label: ALERT: Find out about medicines that should NOT be taken with COMPLERA. A Patient Package Insert for COMPLERA is available for patient information.

Information for Patients

Patients should be advised that:

- Patients should remain under the care of a healthcare provider when using COMPLERA.
- Patients should be informed that COMPLERA is not a cure for HIV infection. Patients should stay on continuous HIV therapy to control HIV infection and decrease HIV-related illnesses. Patients should be told that sustained decreases in plasma HIV RNA have been associated with a reduced risk of progression to AIDS and death.
- Patients should be advised to continue to practice safer sex and to use latex or polyurethane condoms to lower the chance of sexual contact with any body fluids such as semen, vaginal secretions or blood. Patients should be advised never to re-use or share needles.
- Patients should be advised not to breastfeed because at least two of the drugs contained in COMPLERA can be passed to the baby in breast milk. It is not known whether this could harm the baby. Also, mothers with HIV-1 should not breastfeed because HIV-1 can be passed to the baby in breast milk.
- It is important to take COMPLERA on a regular dosing schedule with a meal and to avoid missing doses. A protein drink does not constitute a meal. If the patient misses a dose of COMPLERA within 12 hours of the time it is usually taken, the patient should take COMPLERA with a meal as soon as possible and then take the next dose of COMPLERA at the regularly scheduled time. If a patient misses a dose of COMPLERA by more than 12 hours, the patient should not take the missed dose, but resume the usual dosing schedule. Inform the patient that he or she should not take more or less than the prescribed dose of COMPLERA at any one time.
- Lactic acidosis and severe hepatomegaly with steatosis, including fatal cases, have been reported. Treatment with COMPLERA should be suspended in any patients who develop clinical symptoms suggestive of lactic acidosis or pronounced hepatotoxicity (including nausea, vomiting, unusual or unexpected stomach discomfort, and weakness) [See Warnings and Precautions (5.1)].
- Patients with HIV-1 should be tested for hepatitis B virus (HBV) before initiating antiretroviral therapy. Severe acute exacerbations of hepatitis B have been reported in patients who are coinfected with HBV and HIV-1 and have discontinued EMTRIVA or VIREAD [See Warnings and Precautions (5.2)]. COMPLERA should not be discontinued without first informing their healthcare provider.
- Renal impairment, including cases of acute renal failure and Fanconi syndrome, has been reported in association with the use of VIREAD. COMPLERA should be avoided with concurrent or recent use of a nephrotoxic agent [See Warnings and Precautions (5.3)].
- COMPLERA may interact with many drugs; therefore, patients should be advised to report to their healthcare provider the use of any other prescription or nonprescription medication or herbal products, including St. John's wort [See Warnings and Precautions (5.4)].
- COMPLERA should not be coadministered with the following drugs, as significant decreases in rilpivirine plasma concentrations may occur due to CYP3A enzyme induction or gastric pH increase, which may result in loss of virologic response and possible resistance to COMPLERA or to the class of NNRTIs: the anticonvulsants carbamazepine, oxcarbazepine, phenobarbital, phenytoin; the antimycobacterials rifabutin, rifampin, rifapentine; proton pump inhibitors, such as esomeprazole, lansoprazole, omeprazole, pantoprazole, rabeprazole; the glucocorticoid systemic dexamethasone (more than a single dose); or St. John's wort (Hypericum perforatum) [See Contraindications (4)].
- Patients should be informed that depressive disorders (depressed mood, depression, dysphoria, major depression, mood altered, negative thoughts, suicide attempt, suicidal ideation) have been reported with COMPLERA. If they experience depressive symptoms, they should seek immediate medical evaluation [See Warnings and Precautions (5.5)].
- Patients should be informed that hepatotoxicity has been reported with COMPLERA [See Warnings and Precautions (5.6)].
- Decreases in bone mineral density have been observed with the use of VIREAD. Bone mineral density (BMD) monitoring should be considered in patients who have a history of pathologic bone fracture or other risk factors for osteoporosis or bone loss [See Warnings and Precautions (5.7)].
- COMPLERA should not be coadministered with ATRIPLA, Edurant, EMTRIVA, STRIBILD, TRUVADA, or VIREAD; or with drugs containing lamivudine, including Combivir, Epivir or Epivir-HBV, Epzicom, or Trizivir; or with HEPSERA [See Warnings and Precautions (5.8)].
- Redistribution or accumulation of body fat may occur in patients receiving antiretroviral therapy and that the cause and long-term health effects of these conditions are not known [See Warnings and Precautions (5.9)].
- In some patients with advanced HIV infection (AIDS), signs and symptoms of inflammation from previous infections may occur soon after anti-HIV treatment is started. It is believed that these symptoms are due to an improvement in the body's immune response, enabling the body to fight infections that may have been present with no obvious symptoms. Patients should be advised to inform their healthcare provider immediately of any symptoms of infection [See Warnings and Precautions (5.10)].

Manufactured and distributed by:

Gilead Sciences, Inc.

Foster City, CA 94404

Distributed by:
Physicians Total Care, Inc.
Tulsa, OK 74146

Patient Information

COMPLERA® (kom-PLEH-rah)
(emtricitabine, rilpivirine, tenofovir disoproxil fumarate)
Tablets

Important: Ask your healthcare provider or pharmacist about medicines that should not be taken with COMPLERA. For more information, see the section "What should I tell my healthcare provider before taking COMPLERA?"

Read this Patient Information before you start taking COMPLERA and each time you get a refill. There may be new information. This information does not take the place of talking to your healthcare provider about your medical condition or treatment.

What is the most important information I should know about COMPLERA?

COMPLERA can cause serious side effects, including:

1. Build-up of an acid in your blood (lactic acidosis). Lactic acidosis can happen in some people who take COMPLERA or similar (nucleoside analogs) medicines. Lactic acidosis is a serious medical emergency that can lead to death.
  Lactic acidosis can be hard to identify early, because the symptoms could seem like symptoms of other health problems. Call your healthcare provider right away if you get any of the following symptoms which could be signs of lactic acidosis:
  - feeling very weak or tired
  - have unusual (not normal) muscle pain
  - have trouble breathing
  - have stomach pain with
    - nausea (feel sick to your stomach)
    - vomiting
  - feel cold, especially in your arms and legs
  - feel dizzy or lightheaded
  - have a fast or irregular heartbeat
2. Severe liver problems. Severe liver problems can happen in people who take COMPLERA or similar medicines. In some cases these liver problems can lead to death. Your liver may become large (hepatomegaly) and you may develop fat in your liver (steatosis) when you take COMPLERA.
  Call your healthcare provider right away if you have any of the following symptoms of liver problems:
  - your skin or the white part of your eyes turns yellow (jaundice)
  - dark "tea-colored" urine
  - light-colored bowel movements (stools)
  - loss of appetite for several days or longer
  - nausea
  - stomach pain

You may be more likely to get lactic acidosis or severe liver problems if you are female, very overweight (obese), or have been taking COMPLERA or a similar medicine containing nucleoside analogs for a long time.

3. Worsening of Hepatitis B infection. If you also have hepatitis B virus (HBV) infection and you stop taking COMPLERA, your HBV infection may become worse (flare-up). A "flare-up" is when your HBV infection suddenly returns in a worse way than before. COMPLERA is not approved for the treatment of HBV, so you must discuss your HBV therapy with your healthcare provider.
  - Do not let your COMPLERA run out. Refill your prescription or talk to your healthcare provider before your COMPLERA is all gone.
  - Do not stop taking COMPLERA without first talking to your healthcare provider.
  - If you stop taking COMPLERA, your healthcare provider will need to check your health often and do blood tests regularly to check your HBV infection. Tell your healthcare provider about any new or unusual symptoms you may have after you stop taking COMPLERA.

What is COMPLERA?

COMPLERA is a prescription HIV (Human Immunodeficiency Virus) medicine that:

- is used to treat HIV-1 in adults who have never taken HIV medicines before, and
- who have an amount of HIV in their blood (this is called 'viral load') that is no more than 100,000 copies/mL. Your healthcare provider will measure your viral load.

HIV is the virus that causes AIDS (Acquired Immunodeficiency Syndrome).

COMPLERA contains 3 medicines, (rilpivirine, emtricitabine, tenofovir disoproxil fumarate) combined in one tablet. Emtricitabine (EMTRIVA®) and tenofovir disoproxil fumarate (VIREAD®) are HIV-1 (human immunodeficiency virus) nucleoside analog reverse transcriptase inhibitors (NRTIs). Rilpivirine (Edurant®) is an HIV-1 non-nucleoside analog reverse transcriptase inhibitor (NNRTI).

It is not known if COMPLERA is safe and effective in children under the age of 18 years.

COMPLERA may help:

- Reduce the amount of HIV in your blood.
- Increase the number of white blood cells called CD4+ (T) cells in your blood that help fight off other infections.

Reducing the amount of HIV and increasing the CD4+ (T) cells in your blood may help improve your immune system. This may reduce your risk of death or getting infections that can happen when your immune system is weak (opportunistic infections).

COMPLERA does not cure HIV infections or AIDS.

You must stay on continuous HIV therapy to control HIV infection and decrease HIV-related illnesses.

Avoid doing things that can spread HIV-1 infection to others.

- Do not share or re-use needles or other injection equipment.
- Do not share personal items that can have blood or body fluids on them, like toothbrushes and razor blades.
- Do not have any kind of sex without protection. Always practice safer sex by using a latex or polyurethane condom to lower the chance of sexual contact with any body fluids such as semen, vaginal secretions, or blood.

Ask your healthcare provider if you have any questions about how to prevent passing HIV to other people.

Who should not take COMPLERA?

Do not take COMPLERA if:

- your HIV infection has been previously treated with HIV medicines.
- you are taking any of the following medicines:
  - anti-seizure medicines:
    - carbamazepine (Carbatrol®, Equetro®, Tegretol®, Tegretol- XR®, Teril®, Epitol®)
    - oxcarbazepine (Trileptal®)
    - phenobarbital (Luminal®)
    - phenytoin (Dilantin®, Dilantin-125®, Phenytek®)
  - anti-tuberculosis (anti-TB) medicines:
    - rifabutin (Mycobutin®)
    - rifampin (Rifater®,Rifamate®, Rimactane®, Rifadin®)
    - rifapentine (Priftin®)
  - proton pump inhibitor (PPI) medicine for certain stomach or intestinal problems:
    - dexlansoprazole (Dexilant®)
    - esomeprazole (Nexium®, Vimovo®)
    - lansoprazole (Prevacid®)
    - omeprazole (Prilosec®, Zegerid®)
    - pantoprazole sodium (Protonix®)
    - rabeprazole (Aciphex®)
  - more than 1 dose of the steroid medicine dexamethasone or dexamethasone sodium phosphate
  - St. John's wort (Hypericum perforatum)

What should I tell my healthcare provider before taking COMPLERA?

Before you take COMPLERA, tell your healthcare provider if you:

- have liver problems, including hepatitis B or C virus infection
- have kidney problems
- have ever had a mental health problem
- have bone problems
- are pregnant or plan to become pregnant. It is not known if COMPLERA can harm your unborn child.
  Pregnancy Registry. There is a pregnancy registry for women who take antiviral medicines during pregnancy. The purpose of this registry is to collect information about the health of you and your baby. Talk to your healthcare provider about how you can take part in this registry.
- are breast-feeding or plan to breast-feed. You should not breastfeed if you have HIV because of the risk of passing HIV to your baby. Do not breastfeed if you are taking COMPLERA. At least two of the medicines contained in COMPLERA can be passed to your baby in your breast milk. We do not know whether this could harm your baby. Talk to your healthcare provider about the best way to feed your baby.

Tell your healthcare provider about all the medicines you take, including prescription and nonprescription medicines, vitamins, and herbal supplements.

COMPLERA may affect the way other medicines work, and other medicines may affect how COMPLERA works, and may cause serious side effects. If you take certain medicines with COMPLERA, the amount of COMPLERA in your body may be too low and it may not work to help control your HIV infection. The HIV virus in your body may become resistant to COMPLERA or other HIV medicines that are like it.

COMPLERA provides a complete treatment for HIV infection. Do not take other HIV medicines with COMPLERA.

If you take COMPLERA, you should not take:

- other medicines that contain tenofovir (VIREAD, TRUVADA®, STRIBILD™, ATRIPLA®)
- other medicines that contain emtricitabine or lamivudine (EMTRIVA, Combivir®, Epivir® or Epivir-HBV®, Epzicom®, Trizivir®, ATRIPLA, TRUVADA, STRIBILD)
- rilpivirine (Edurant)
- adefovir (HEPSERA®)

Especially tell your healthcare provider if you take:

- an antacid medicine that contains aluminum, magnesium hydroxide, or calcium carbonate. If you take an antacid during treatment with COMPLERA, take the antacid at least 2 hours before or at least 4 hours after you take COMPLERA.
- a medicine to block the acid in your stomach, including cimetidine (Tagamet®), famotidine (Pepcid®), nizatidine (Axid®), or ranitidine hydrochloride (Zantac®). If you take one of these medicines during treatment with COMPLERA, take the acid blocker at least 12 hours before or at least 4 hours after you take COMPLERA.
- any of these medicines (if taken by mouth or injection):
  - clarithromycin (Biaxin®)
  - erythromycin (E-Mycin®, Eryc®, Ery-Tab®, PCE®, Pediazole®, Iloson®)
  - fluconazole (Diflucan®)
  - itraconazole (Sporanox®)
  - ketoconazole (Nizoral®)
  - methadone (Dolophine®)
  - posaconazole (Noxafil®)
  - telithromycin (Ketek®)
  - voriconazole (Vfend®)
- medicines that are eliminated by the kidney, including acyclovir (Zovirax®), cidofovir (VISTIDE®), ganciclovir (Cytovene IV®, Vitrasert®), valacyclovir (Valtrex®), and valganciclovir (Valcyte®)

Ask your healthcare provider or pharmacist if you are not sure if your medicine is one that is listed above.

Know the medicines you take. Keep a list of your medicines and show it to your healthcare provider and pharmacist when you get a new medicine. Your healthcare provider and your pharmacist can tell you if you can take these medicines with COMPLERA. Do not start any new medicines while you are taking COMPLERA without first talking with your healthcare provider or pharmacist. You can ask your healthcare provider or pharmacist for a list of medicines that can interact with COMPLERA.

How should I take COMPLERA?

- Stay under the care of your healthcare provider during treatment with COMPLERA.
- Take COMPLERA exactly as your healthcare provider tells you to take it.
- Always take COMPLERA with a meal. Taking COMPLERA with a meal is important to help get the right amount of medicine in your body. A protein drink does not replace a meal.
- Do not change your dose or stop taking COMPLERA without first talking with your healthcare provider. See your healthcare provider regularly while taking COMPLERA.
- If you miss a dose of COMPLERA within 12 hours of the time you usually take it, take your dose of COMPLERA with a meal as soon as possible. Then, take your next dose of COMPLERA at the regularly scheduled time. If you miss a dose of COMPLERA by more than 12 hours of the time you usually take it, wait and then take the next dose of COMPLERA at the regularly scheduled time.
- Do not take more than your prescribed dose to make up for a missed dose.
- When your COMPLERA supply starts to run low, get more from your healthcare provider or pharmacy. It is very important not to run out of COMPLERA. The amount of virus in your blood may increase if the medicine is stopped for even a short time.
- If you take too much COMPLERA, contact your local poison control center or go to the nearest hospital emergency room right away.

What are the possible side effects of COMPLERA?

COMPLERA can cause serious side effects, including:

- See "What is the most important information I should know about COMPLERA?"
- New or worse kidney problems, including kidney failure, can happen in some people who take COMPLERA. Your healthcare provider should do blood tests to check your kidneys before starting treatment with COMPLERA. If you have had kidney problems in the past or need to take another medicine that can cause kidney problems, your healthcare provider may need to do blood tests to check your kidneys during your treatment with COMPLERA.
- Depression or mood changes. Tell your healthcare provider right away if you have any of the following symptoms:
  - feeling sad or hopeless
  - feeling anxious or restless
  - have thoughts of hurting yourself (suicide) or have tried to hurt yourself
- Change in liver enzymes. People with a history of hepatitis B or C virus infection or who have certain liver enzyme changes may have an increased risk of developing new or worsening liver problems during treatment with COMPLERA. Liver problems can also happen during treatment with COMPLERA in people without a history of liver disease. Your healthcare provider may need to do tests to check your liver enzymes before and during treatment with COMPLERA.
- Bone problems can happen in some people who take COMPLERA. Bone problems include bone pain, softening or thinning (which may lead to fractures). Your healthcare provider may need to do additional tests to check your bones.
- Changes in body fat can happen in people taking HIV medicine. These changes may include increased amount of fat in the upper back and neck ("buffalo hump"), breast, and around the main part of your body (trunk). Loss of fat from the legs, arms and face may also happen. The cause and long term health effect of these conditions are not known.
- Changes in your immune system (Immune Reconstitution Syndrome) can happen when you start taking HIV medicines. Your immune system may get stronger and begin to fight infections that have been hidden in your body for a long time. Tell your healthcare provider if you start having new symptoms after starting your HIV medicine.

The most common side effects of COMPLERA include:

- trouble sleeping (insomnia)
- abnormal dreams
- headache
- dizziness
- diarrhea
- nausea
- rash
- tiredness
- depression

Additional common side effects include:

- vomiting
- stomach pain or discomfort
- skin discoloration (small spots or freckles)
- pain

Tell your healthcare provider if you have any side effect that bothers you or that does not go away.

These are not all the possible side effects of COMPLERA. For more information, ask your healthcare provider or pharmacist.

Call your doctor for medical advice about side effects. You may report side effects to FDA at 1-800-FDA-1088 (1-800-332-1088).

How do I store COMPLERA?

- Store COMPLERA at room temperature between 68 °F to 77 °F (20 °C to 25 °C).
- Keep COMPLERA in its original container and keep the container tightly closed.
- Do not use COMPLERA if the seal over the bottle opening is broken or missing.

Keep COMPLERA and all other medicines out of reach of children.

General information about COMPLERA:

Medicines are sometimes prescribed for purposes other than those listed in a Patient Information leaflet. Do not use COMPLERA for a condition for which it was not prescribed. Do not give COMPLERA to other people, even if they have the same symptoms you have. It may harm them.

This leaflet summarizes the most important information about COMPLERA. If you would like more information, talk with your healthcare provider. You can ask your healthcare provider or pharmacist for information about COMPLERA that is written for health professionals. For more information, call 1-800-445-3235 or go to www.COMPLERA.com.

What are the ingredients of COMPLERA?

Active ingredients: emtricitabine, rilpivirine hydrochloride, and tenofovir disoproxil fumarate

Inactive ingredients: pregelatinized starch, lactose monohydrate, microcrystalline cellulose, croscarmellose sodium, magnesium stearate, povidone, polysorbate 20. The tablet film coating contains polyethylene glycol, hypromellose, lactose monohydrate, triacetin, titanium dioxide, iron oxide red, FD&C Blue #2 aluminum lake, FD&C Yellow #6 aluminum lake.

This Patient Information has been approved by the U.S. Food and Drug Administration

Manufactured and distributed by:

Gilead Sciences, Inc.

Foster City, CA 94404

Revised: January 2013

COMPLERA, EMTRIVA, HEPSERA, TRUVADA, VIREAD, and VISTIDE are trademarks of Gilead Sciences, Inc., or its related companies. Edurant is a trademark of Janssen Pharmaceuticals, Inc. ATRIPLA is a trademark of Bristol-Myers Squibb & Gilead Sciences, LLC. All other trademarks referenced herein are the property of their respective owners.

202123-GS-002

PRINCIPAL DISPLAY PANEL - Representative Label

NDC 54868-6360-0
30 tablets

COMPLERA™
(emtricitabine, rilpivirine,
tenofovir disoproxil fumarate) Tablets
200 mg/25 mg/300 mg

Note to pharmacist: Do not cover ALERT box with pharmacy label.

ALERT: Find out about medicines that
should NOT be taken with COMPLERA™